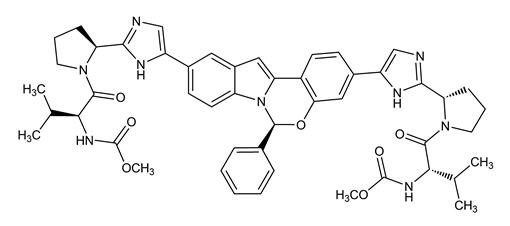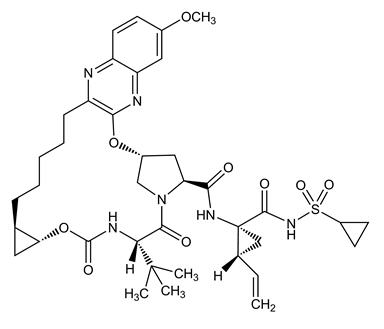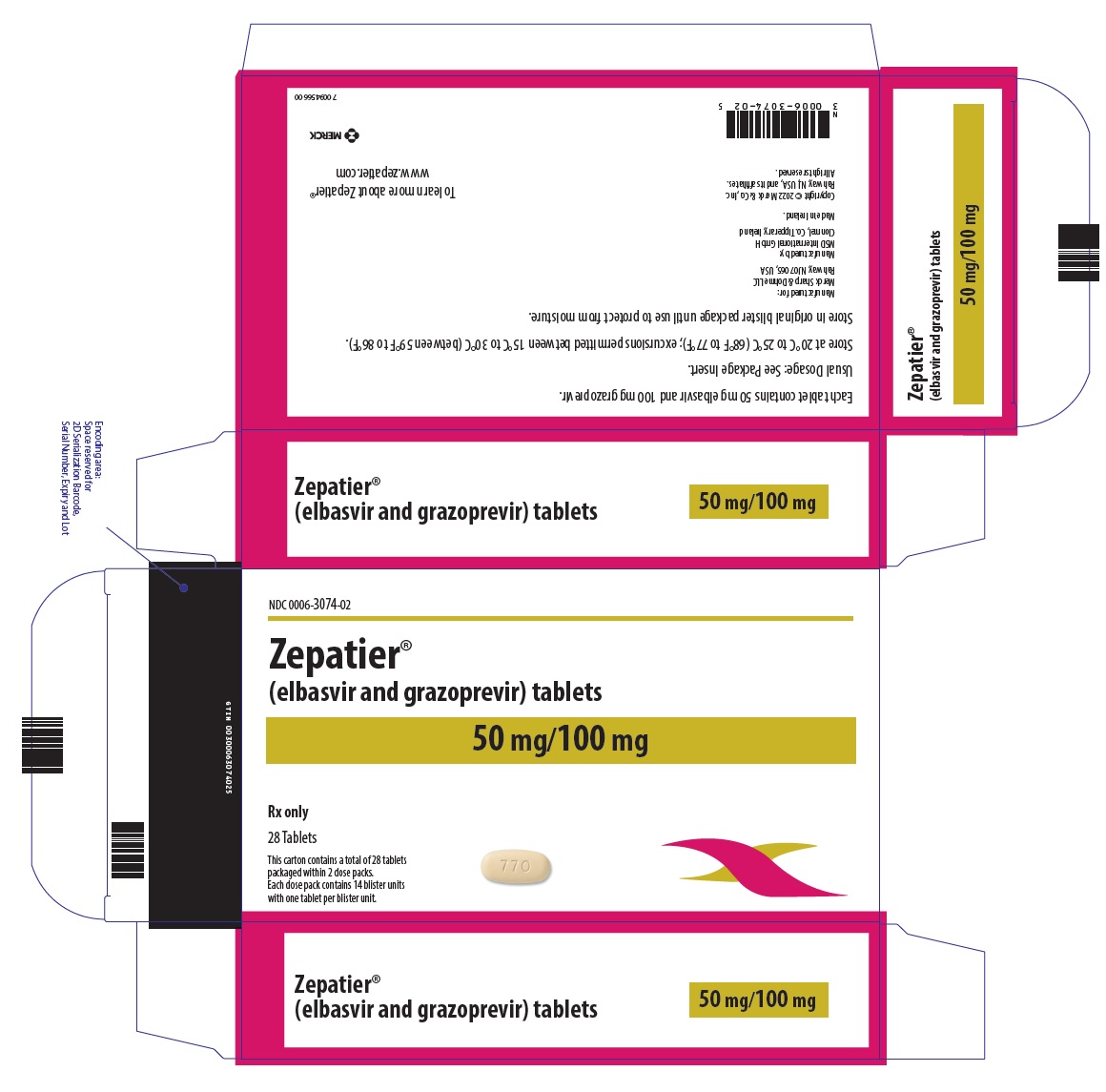 DRUG LABEL: ZEPATIER
NDC: 0006-3074 | Form: TABLET, FILM COATED
Manufacturer: Merck Sharp & Dohme LLC
Category: prescription | Type: HUMAN PRESCRIPTION DRUG LABEL
Date: 20240705

ACTIVE INGREDIENTS: ELBASVIR 50 mg/1 1; GRAZOPREVIR ANHYDROUS 100 mg/1 1
INACTIVE INGREDIENTS: SILICON DIOXIDE; COPOVIDONE K25-31; CROSCARMELLOSE SODIUM; HYPROMELLOSE 2910 (3 MPA.S); LACTOSE MONOHYDRATE; MAGNESIUM STEARATE; MANNITOL; MICROCRYSTALLINE CELLULOSE; SODIUM CHLORIDE; SODIUM LAURYL SULFATE; TOCOPHERSOLAN; CARNAUBA WAX; FERROSOFERRIC OXIDE; HYPROMELLOSE 2910 (15 MPA.S); FERRIC OXIDE RED; FERRIC OXIDE YELLOW; TITANIUM DIOXIDE; TRIACETIN

HIGHLIGHTS OF PRESCRIBING INFORMATION

These highlights do not include all the information needed to use ZEPATIER safely and effectively. See full prescribing information for ZEPATIER.
ZEPATIER® (elbasvir and grazoprevir) tablets, for oral use
Initial U.S. Approval: 2016

WARNING: RISK OF HEPATITIS B VIRUS REACTIVATION IN PATIENTS COINFECTED WITH HCV AND HBV

See full prescribing information for complete boxed warning.

Hepatitis B virus (HBV) reactivation has been reported, in some cases resulting in fulminant hepatitis, hepatic failure, and death. (5.1)

RECENT MAJOR CHANGES

Indications and Usage (1) | 12/2021
Dosage and Administration, Recommended Dosage in Adult and Pediatric Patients 12 Years of Age and Older or Weighing at Least 30 kg (2.2) | 12/2021

1 INDICATIONS AND USAGE

ZEPATIER is a fixed-dose combination product containing elbasvir, a hepatitis C virus (HCV) NS5A inhibitor, and grazoprevir, an HCV NS3/4A protease inhibitor, and is indicated for treatment of chronic HCV genotype 1 or 4 infection in adult and pediatric patients 12 years of age and older or weighing at least 30 kg. ZEPATIER is indicated for use with ribavirin in certain patient populations. (1)

2 DOSAGE AND ADMINISTRATION

- Testing Prior to Initiation of Therapy:
  - Test all patients for HBV infection by measuring HBsAg and anti-HBc. (2.1)
  - Genotype 1a: Testing for the presence of virus with NS5A resistance-associated polymorphisms is recommended. (2.1)
  - Obtain hepatic laboratory testing. (2.1)
- Recommended dosage in adult and pediatric patients 12 years of age and older or weighing at least 30 kg: One tablet taken orally once daily with or without food. (2.2)

Dosage Regimens and Durations for ZEPATIER in Patients with Genotype 1 or 4 HCV with or without Cirrhosis
Patient Population | Treatment | Duration
Genotype 1a: Treatment-naïve or PegIFN/RBV-experienced [Peginterferon alfa + ribavirin.] without baseline NS5A polymorphisms [Polymorphisms at amino acid positions 28, 30, 31, or 93.] | ZEPATIER | 12 weeks
Genotype 1a: Treatment-naïve or PegIFN/RBV-experienced with baseline NS5A polymorphisms | ZEPATIER + ribavirin | 16 weeks
Genotype 1b: Treatment-naïve or PegIFN/RBV-experienced | ZEPATIER | 12 weeks
Genotype 1a or 1b: PegIFN/RBV/PI-experienced [Peginterferon alfa + ribavirin + HCV NS3/4A protease inhibitor.] | ZEPATIER + ribavirin | 12 weeks
Genotype 4: Treatment-naïve | ZEPATIER | 12 weeks
Genotype 4: PegIFN/RBV-experienced | ZEPATIER + ribavirin | 16 weeks

- HCV/HIV-1 co-infection: Follow the dosage recommendations in the table above. (2.2)
- Renal Impairment, including hemodialysis: No dosage adjustment of ZEPATIER is recommended. Refer to ribavirin prescribing information for ribavirin dosing and dosage modifications. (2.3)

3 DOSAGE FORMS AND STRENGTHS

- Tablets: 50 mg elbasvir and 100 mg grazoprevir (3)

4 CONTRAINDICATIONS

- Patients with moderate or severe hepatic impairment (Child-Pugh B or C). (4)
- OATP1B1/3 inhibitors that are known or expected to significantly increase grazoprevir plasma concentrations, strong CYP3A inducers, and efavirenz. (4)
- If ZEPATIER is administered with ribavirin, the contraindications to ribavirin also apply. (4)

5 WARNINGS AND PRECAUTIONS

- Risk of Hepatitis B Virus Reactivation: Test all patients for evidence of current or prior HBV infection before initiation of HCV treatment. Monitor HCV/HBV coinfected patients for HBV reactivation and hepatitis flare during HCV treatment and post-treatment follow-up. Initiate appropriate patient management for HBV infection as clinically indicated. (5.1)
- ALT Elevations: Perform hepatic laboratory testing prior to therapy, at treatment week 8, and as clinically indicated. For patients receiving 16 weeks of therapy, perform additional hepatic laboratory testing at treatment week 12. For ALT elevations on ZEPATIER, follow recommendations in full prescribing information. (5.2)
- Risk of Hepatic Decompensation/Failure in Patients with Evidence of Advanced Liver Disease: Hepatic decompensation/failure, including fatal outcomes, have been reported mostly in patients with cirrhosis and baseline moderate or severe liver impairment (Child-Pugh B or C) treated with HCV NS3/4A protease inhibitor-containing regimens. Monitor for clinical and laboratory evidence of hepatic decompensation. Discontinue ZEPATIER in patients who develop evidence of hepatic decompensation/failure. (5.3)
- Risk Associated with Ribavirin Combination Treatment: If ZEPATIER is administered with ribavirin, the warnings and precautions for ribavirin also apply. (5.4)

6 ADVERSE REACTIONS

In subjects receiving ZEPATIER for 12 weeks, the most commonly reported adverse reactions of all intensity (greater than or equal to 5% in placebo-controlled trials) were fatigue, headache, and nausea. In subjects receiving ZEPATIER with ribavirin for 16 weeks, the most commonly reported adverse reactions of moderate or severe intensity (greater than or equal to 5%) were anemia and headache. (6.1)

To report SUSPECTED ADVERSE REACTIONS, contact Merck Sharp & Dohme LLC at 1-877-888-4231 or FDA at 1-800-FDA-1088 or www.fda.gov/medwatch .

7 DRUG INTERACTIONS

- Co-administration of ZEPATIER with moderate CYP3A inducers is not recommended as they may decrease the plasma concentration of ZEPATIER. (7)
- Co-administration of ZEPATIER with certain strong CYP3A inhibitors is not recommended as they may increase the plasma concentration of ZEPATIER. (7)
- Clearance of HCV infection with direct-acting antivirals may lead to changes in hepatic function, which may impact safe and effective use of concomitant medications. Frequent monitoring of relevant laboratory parameters (INR or blood glucose) and dose adjustments of certain concomitant medications may be necessary. (7.2)
- Consult the full prescribing information prior to and during treatment for potential drug interactions. (4, 5.5, 7, 12.3)

FULL PRESCRIBING INFORMATION

WARNING: RISK OF HEPATITIS B VIRUS REACTIVATION IN PATIENTS COINFECTED WITH HCV AND HBV

Test all patients for evidence of current or prior hepatitis B virus (HBV) infection before initiating treatment with ZEPATIER. HBV reactivation has been reported in HCV/HBV coinfected patients who were undergoing or had completed treatment with HCV direct acting antivirals and were not receiving HBV antiviral therapy. Some cases have resulted in fulminant hepatitis, hepatic failure, and death. Monitor HCV/HBV coinfected patients for hepatitis flare or HBV reactivation during HCV treatment and post-treatment follow-up. Initiate appropriate patient management for HBV infection as clinically indicated [see Warnings and Precautions (5.1)].

1 INDICATIONS AND USAGE

ZEPATIER® is indicated for the treatment of chronic hepatitis C virus (HCV) genotype 1 or 4 infection in adult and pediatric patients 12 years of age and older or weighing at least 30 kg.

ZEPATIER is indicated for use with ribavirin in certain patient populations [see Dosage and Administration (2.2)].

2 DOSAGE AND ADMINISTRATION

2.1 Testing Prior to the Initiation of Therapy

Testing for HBV Infection

Test all patients for evidence of current or prior HBV infection by measuring hepatitis B surface antigen (HBsAg) and hepatitis B core antibody (anti-HBc) before initiating HCV treatment with ZEPATIER [see Warnings and Precautions (5.1)].

NS5A Resistance Testing in HCV Genotype 1a-Infected Patients

Testing patients with HCV genotype 1a infection for the presence of virus with NS5A resistance-associated polymorphisms is recommended prior to initiation of treatment with ZEPATIER to determine dosage regimen and duration [see Dosage and Administration (2.2), Table 1]. In subjects receiving ZEPATIER for 12 weeks, sustained virologic response (SVR12) rates were lower in genotype 1a-infected patients with one or more baseline NS5A resistance-associated polymorphisms at amino acid positions 28, 30, 31, or 93 [see Microbiology (12.4), Table 12].

Hepatic Laboratory Testing

Obtain hepatic laboratory testing prior to and during treatment with ZEPATIER [see Warnings and Precautions (5.2, 5.3)].

2.2 Recommended Dosage in Adult and Pediatric Patients 12 Years of Age and Older or Weighing at Least 30 kg

ZEPATIER is a two-drug, fixed-dose combination product containing 50 mg of elbasvir and 100 mg of grazoprevir in a single tablet. The recommended dosage of ZEPATIER is one tablet taken orally once daily with or without food [see Clinical Pharmacology (12.3)]. ZEPATIER is used in combination with ribavirin in certain patient populations (see Table 1). When administered with ZEPATIER, the recommended dosage of ribavirin in patients without renal impairment is weight-based administered in two divided doses with food. For further information on ribavirin dosing and dosage modifications, refer to the ribavirin prescribing information.

Treatment Regimen and Duration of Therapy

Relapse rates are affected by baseline host and viral factors and differ between treatment regimens and durations for certain subgroups [see Clinical Studies (14)].

Table 1 below provides the recommended ZEPATIER treatment regimen and duration based on the patient population and genotype in HCV mono-infected and HCV/HIV-1 co-infected patients with or without cirrhosis and with or without renal impairment including patients receiving hemodialysis.

Table 1: Recommended Dosage Regimens and Durations for ZEPATIER for Treatment of HCV Genotype 1 or 4 in Patients with or without Cirrhosis
Patient Population | Treatment | Duration
Genotype 1a: Treatment-naïve or PegIFN/RBV-experienced [Patients who have failed treatment with peginterferon alfa (PegIFN) + ribavirin (RBV).] without baseline NS5A polymorphisms [NS5A resistance-associated polymorphisms at amino acid positions 28, 30, 31, or 93. See section 2.1 Testing prior to the initiation of therapy, subsection NS5A resistance testing in HCV genotype 1a-infected patients.] | ZEPATIER | 12 weeks
Genotype 1a: Treatment-naïve or PegIFN/RBV-experienced with baseline NS5A polymorphisms | ZEPATIER + RBV [For patients with CrCl greater than 50 mL per minute, the recommended dosage of ribavirin is weight-based (less than 66 kg = 800 mg per day, 66 to 80 kg = 1000 mg per day, 81 to 105 kg = 1200 mg per day, greater than 105 kg = 1400 mg per day) administered in two divided doses with food. For patients with CrCl less than or equal to 50 mL per minute, including patients receiving hemodialysis, refer to the ribavirin tablet prescribing information for the correct ribavirin dosage. In pediatric patients, the dosing for ribavirin is weight-based in two divided doses. Refer to the ribavirin tablet prescribing information for the correct ribavirin dosage regimen.] | 16 weeks
Genotype 1b: Treatment-naïve or PegIFN/RBV-experienced | ZEPATIER | 12 weeks
Genotype 1a [The optimal ZEPATIER-based treatment regimen and duration of therapy for PegIFN/RBV/PI-experienced genotype 1a-infected patients with one or more baseline NS5A resistance-associated polymorphisms at positions 28, 30, 31, and 93 has not been established.] or 1b: PegIFN/RBV/PI-experienced [Patients who have failed treatment with PegIFN + RBV + HCV NS3/4A protease inhibitor (PI): boceprevir, simeprevir, or telaprevir.] | ZEPATIER + RBV | 12 weeks
Genotype 4: Treatment-Naïve | ZEPATIER | 12 weeks
Genotype 4: PegIFN/RBV-experienced | ZEPATIER + RBV | 16 weeks

2.3 Renal Impairment

No dosage adjustment of ZEPATIER is recommended in patients with any degree of renal impairment including patients on hemodialysis. Administer ZEPATIER with or without ribavirin according to the recommendations in Table 1 [see Use in Specific Populations (8.8) and Clinical Studies (14.4)]. Refer to the ribavirin tablet prescribing information for the correct ribavirin dosage for patients with CrCl less than or equal to 50 mL per minute.

2.4 Hepatic Impairment

No dosage adjustment of ZEPATIER is recommended in patients with mild hepatic impairment (Child-Pugh A). ZEPATIER is contraindicated in patients with moderate or severe hepatic impairment (Child-Pugh B or C) or those with any history of prior hepatic decompensation [see Contraindications (4), Warnings and Precautions (5.3), Use in Specific Populations (8.9), and Clinical Pharmacology (12.3)].

3 DOSAGE FORMS AND STRENGTHS

ZEPATIER is available as a beige-colored, oval-shaped, film-coated tablet debossed with "770" on one side and plain on the other. Each tablet contains 50 mg elbasvir and 100 mg grazoprevir.

4 CONTRAINDICATIONS

- ZEPATIER is contraindicated in patients with moderate or severe hepatic impairment (Child-Pugh B or C) due to the expected significantly increased grazoprevir plasma concentration and the increased risk of alanine aminotransferase (ALT) elevations [see Warnings and Precautions (5.2), Use in Specific Populations (8.9), and Clinical Pharmacology (12.3)].
- ZEPATIER is contraindicated in patients with moderate or severe hepatic impairment (Child-Pugh B or C) or those with any history of hepatic decompensation due to the risk of hepatic decompensation [see Warnings and Precautions (5.3), Use in Specific Populations (8.9)].
- ZEPATIER is contraindicated with inhibitors of organic anion transporting polypeptides 1B1/3 (OATP1B1/3) that are known or expected to significantly increase grazoprevir plasma concentrations, strong inducers of cytochrome P450 3A (CYP3A), and efavirenz [see Warnings and Precautions (5.5), Drug Interactions (7), and Clinical Pharmacology (12.3)].
- If ZEPATIER is administered with ribavirin, the contraindications to ribavirin also apply to this combination regimen. Refer to the ribavirin prescribing information for a list of contraindications for ribavirin.

Table 2 lists drugs that are contraindicated with ZEPATIER.

Table 2: Drugs that are Contraindicated with ZEPATIER
Drug Class | Drug(s) within Class that are Contraindicated | Clinical Comment [This table is not a comprehensive list of all drugs that strongly induce CYP3A. This table may not include all OATP1B1/3 inhibitors that significantly increase grazoprevir plasma concentrations.]
Anticonvulsants | Phenytoin Carbamazepine | May lead to loss of virologic response to ZEPATIER due to significant decreases in elbasvir and grazoprevir plasma concentrations caused by strong CYP3A induction.
Antimycobacterials | Rifampin | May lead to loss of virologic response to ZEPATIER due to significant decreases in elbasvir and grazoprevir plasma concentrations caused by strong CYP3A induction.
Herbal Products | St. John's Wort (Hypericum perforatum) | May lead to loss of virologic response to ZEPATIER due to significant decreases in elbasvir and grazoprevir plasma concentrations caused by strong CYP3A induction.
HIV Medications | Efavirenz [Efavirenz is included as a strong CYP3A inducer in this table, since co-administration reduced grazoprevir exposure by ≥80% [see Table 9].] | May lead to loss of virologic response to ZEPATIER due to significant decreases in elbasvir and grazoprevir plasma concentrations caused by CYP3A induction.
HIV Medications | Atazanavir Darunavir Lopinavir Saquinavir Tipranavir | May increase the risk of ALT elevations due to a significant increase in grazoprevir plasma concentrations caused by OATP1B1/3 inhibition.
Immunosuppressants | Cyclosporine | May increase the risk of ALT elevations due to a significant increase in grazoprevir plasma concentrations caused by OATP1B1/3 inhibition.

5 WARNINGS AND PRECAUTIONS

5.1 Risk of Hepatitis B Virus Reactivation in Patients Coinfected with HCV and HBV

Hepatitis B virus (HBV) reactivation has been reported in HCV/HBV coinfected patients who were undergoing or had completed treatment with HCV direct acting antivirals, and who were not receiving HBV antiviral therapy. Some cases have resulted in fulminant hepatitis, hepatic failure and death. Cases have been reported in patients who are HBsAg positive and also in patients with serologic evidence of resolved HBV infection (i.e., HBsAg negative and anti-HBc positive). HBV reactivation has also been reported in patients receiving certain immunosuppressant or chemotherapeutic agents; the risk of HBV reactivation associated with treatment with HCV direct-acting antivirals may be increased in these patients.

HBV reactivation is characterized as an abrupt increase in HBV replication manifesting as a rapid increase in serum HBV DNA level. In patients with resolved HBV infection reappearance of HBsAg can occur. Reactivation of HBV replication may be accompanied by hepatitis, i.e., increases in aminotransferase levels and, in severe cases, increases in bilirubin levels, liver failure, and death can occur.

Test all patients for evidence of current or prior HBV infection by measuring HBsAg and anti-HBc before initiating HCV treatment with ZEPATIER. In patients with serologic evidence of HBV infection, monitor for clinical and laboratory signs of hepatitis flare or HBV reactivation during HCV treatment with ZEPATIER and during post-treatment follow-up. Initiate appropriate patient management for HBV infection as clinically indicated.

5.2 Increased Risk of ALT Elevations

During clinical trials with ZEPATIER with or without ribavirin, 1% of subjects experienced elevations of ALT from normal levels to greater than 5 times the upper limit of normal (ULN), generally at or after treatment week 8. ALT elevations were typically asymptomatic and most resolved with ongoing or completion of therapy. Higher rates of late ALT elevations occurred in the following subpopulations: female sex (2% [10/608]), Asian race (2% [4/164]), and age 65 years or older (2% [3/177]) [see Adverse Reactions (6.1)].

Hepatic laboratory testing should be performed prior to therapy, at treatment week 8, and as clinically indicated. For patients receiving 16 weeks of therapy, additional hepatic laboratory testing should be performed at treatment week 12.

- Patients should be instructed to consult their healthcare professional without delay if they have onset of fatigue, weakness, lack of appetite, nausea and vomiting, jaundice, or discolored feces.
- Consider discontinuing ZEPATIER if ALT levels remain persistently greater than 10 times the ULN.
- Discontinue ZEPATIER if ALT elevation is accompanied by signs or symptoms of liver inflammation or increasing conjugated bilirubin, alkaline phosphatase, or International Normalized Ratio (INR).

5.3 Risk of Hepatic Decompensation/Failure in Patients with Evidence of Advanced Liver Disease

Postmarketing cases of hepatic decompensation/failure, including those with fatal outcomes, have been reported in patients treated with HCV NS3/4A protease inhibitor-containing regimens, including ZEPATIER.

Reported cases occurred in patients treated with HCV NS3/4A protease inhibitor-containing regimens with baseline cirrhosis with and without moderate or severe liver impairment (Child-Pugh B or C) as well as some patients without cirrhosis. Because these events are reported voluntarily from a population of uncertain size, it is not always possible to reliably estimate their frequency or establish a causal relationship to drug exposure.

Hepatic laboratory testing should be performed in all patients [see Warnings and Precautions (5.2)]. In patients with compensated cirrhosis (Child-Pugh A) or evidence of advanced liver disease, such as portal hypertension, more frequent hepatic laboratory testing may be warranted; and patients should be monitored for signs and symptoms of hepatic decompensation such as the presence of jaundice, ascites, hepatic encephalopathy, and variceal hemorrhage. Discontinue ZEPATIER in patients who develop evidence of hepatic decompensation/failure.

ZEPATIER is contraindicated in patients with moderate to severe hepatic impairment (Child-Pugh B or C) or those with any history of prior hepatic decompensation [see Contraindications (4), Adverse Reactions (6.1), Use in Specific Populations (8.9), and Clinical Pharmacology (12.3)].

5.4 Risks Associated with Ribavirin Combination Treatment

If ZEPATIER is administered with ribavirin, the warnings and precautions for ribavirin, including the pregnancy avoidance warning, also apply to this combination regimen. Refer to the ribavirin prescribing information for a full list of warnings and precautions for ribavirin [see Dosage and Administration (2.2)].

5.5 Risk of Adverse Reactions or Reduced Therapeutic Effect Due to Drug Interactions

The concomitant use of ZEPATIER and certain drugs may result in known or potentially significant drug interactions, some of which may lead to:

- Possible clinically significant adverse reactions from greater exposure of concomitant drugs or components of ZEPATIER.
- Significant decrease of elbasvir and grazoprevir plasma concentrations which may lead to reduced therapeutic effect of ZEPATIER and possible development of resistance.

See Tables 2 and 6 for steps to prevent or manage these known or potentially significant drug interactions, including dosing recommendations [see Contraindications (4) and Drug Interactions (7.2)].

6 ADVERSE REACTIONS

The following adverse reaction is described below and elsewhere in the labeling:

- Increased Risk of ALT Elevations [see Warnings and Precautions (5.2)].

6.1 Clinical Trials Experience

Because clinical trials are conducted under widely varying conditions, adverse reaction rates observed in the clinical trials of a drug cannot be directly compared to rates in the clinical trials of another drug and may not reflect the rates observed in practice.

If ZEPATIER is administered with ribavirin, refer to the prescribing information for ribavirin for a description of ribavirin-associated adverse reactions.

Clinical Trials in Adult Subjects

The safety of ZEPATIER in adult subjects was assessed based on 2 placebo-controlled trials and 7 uncontrolled Phase 2 and 3 clinical trials in approximately 1700 subjects with chronic hepatitis C virus infection with compensated liver disease (with or without cirrhosis) [see Clinical Studies (14)].

Adverse Reactions with ZEPATIER in Treatment-Naïve Subjects

C-EDGE TN was a Phase 3 randomized, double-blind, placebo-controlled trial in 421 treatment-naïve (TN) subjects with HCV infection who received ZEPATIER or placebo one tablet once daily for 12 weeks. Adverse reactions (all intensity) occurring in C-EDGE TN in at least 5% of subjects treated with ZEPATIER for 12 weeks are presented in Table 3. In subjects treated with ZEPATIER who reported an adverse reaction, 73% had adverse reactions of mild severity. The type and severity of adverse reactions in subjects with compensated cirrhosis were comparable to those seen in subjects without cirrhosis. No subjects treated with ZEPATIER or placebo had serious adverse reactions. The proportion of subjects treated with ZEPATIER or placebo who permanently discontinued treatment due to adverse reactions was 1% in each group.

Table 3: Adverse Reactions (All Intensity) Reported in ≥5% of Treatment-Naïve Subjects with HCV Treated with ZEPATIER for 12 Weeks in C-EDGE TN
 | C-EDGE TN
 | ZEPATIER N=316 % 12 weeks | Placebo N=105 % 12 weeks
Fatigue | 11% | 10%
Headache | 10% | 9%

C-EDGE COINFECTION was a Phase 3 open-label trial in 218 treatment-naïve HCV/HIV co-infected subjects who received ZEPATIER one tablet once daily for 12 weeks. Adverse reactions (all intensity) reported in C-EDGE COINFECTION in at least 5% of subjects treated with ZEPATIER for 12 weeks were fatigue (7%), headache (7%), nausea (5%), insomnia (5%), and diarrhea (5%). No subjects reported serious adverse reactions or discontinued treatment due to adverse reactions. No subjects switched their antiretroviral therapy regimen due to loss of plasma HIV-1 RNA suppression. Median increase in CD4+ T-cell counts of 31 cells per mm^3 was observed at the end of 12 weeks of treatment.

Adverse Reactions with ZEPATIER with or without Ribavirin in Treatment-Experienced Subjects

C-EDGE TE was a Phase 3 randomized, open-label trial in treatment-experienced (TE) subjects. Adverse reactions of moderate or severe intensity reported in C-EDGE TE in at least 2% of subjects treated with ZEPATIER one tablet once daily for 12 weeks or ZEPATIER one tablet once daily with ribavirin for 16 weeks are presented in Table 4. No subjects treated with ZEPATIER without ribavirin for 12 weeks reported serious adverse reactions or discontinued treatment due to adverse reactions. The proportion of subjects treated with ZEPATIER with ribavirin for 16 weeks with serious adverse reactions was 1%. The proportion of subjects treated with ZEPATIER with ribavirin for 16 weeks who permanently discontinued treatment due to adverse reactions was 3%. The type and severity of adverse reactions in subjects with cirrhosis were comparable to those seen in subjects without cirrhosis.

Table 4: Adverse Reactions (Moderate or Severe Intensity) Reported in ≥2% of PegIFN/RBV-Experienced Subjects with HCV Treated with ZEPATIER for 12 Weeks or ZEPATIER + Ribavirin for 16 Weeks in C-EDGE TE
 | C-EDGE TE
 | ZEPATIER N=105 % 12 weeks | ZEPATIER + Ribavirin N=106 % 16 weeks
Anemia | 0% | 8%
Headache | 0% | 6%
Fatigue | 5% | 4%
Dyspnea | 0% | 4%
Rash or Pruritus | 0% | 4%
Irritability | 1% | 3%
Abdominal pain | 2% | 2%
Depression | 1% | 2%
Arthralgia | 0% | 2%
Diarrhea | 2% | 0%

The type and severity of adverse reactions with ZEPATIER with or without ribavirin in 10 treatment-experienced subjects with HCV/HIV co-infection were comparable to those reported in subjects without HIV co-infection. Median increase in CD4+ T-cell counts of 32 cells/mm^3 was observed at the end of 12 weeks of treatment with ZEPATIER alone. In subjects treated with ZEPATIER with ribavirin for 16 weeks, CD4+ T-cell counts decreased a median of 135 cells per mm^3 at the end of treatment. No subjects switched their antiretroviral therapy regimen due to loss of plasma HIV-1 RNA suppression. No subject experienced an AIDS-related opportunistic infection.

C-SALVAGE was a Phase 2 open-label trial in 79 PegIFN/RBV/PI-experienced subjects. Adverse reactions of moderate or severe intensity reported in C-SALVAGE in at least 2% of subjects treated with ZEPATIER once daily with ribavirin for 12 weeks were fatigue (3%) and insomnia (3%). No subjects reported serious adverse reactions or discontinued treatment due to adverse reactions.

Adverse Reactions with ZEPATIER in Subjects with Severe Renal Impairment including Subjects on Hemodialysis

The safety of elbasvir and grazoprevir in comparison to placebo in subjects with severe renal impairment (Stage 4 or Stage 5 chronic kidney disease, including subjects on hemodialysis) and chronic hepatitis C virus infection with compensated liver disease (with or without cirrhosis) was assessed in 235 subjects (C-SURFER) [see Clinical Studies (14.4)]. The adverse reactions (all intensity) occurring in at least 5% of subjects treated with ZEPATIER for 12 weeks are presented in Table 5. In subjects treated with ZEPATIER who reported an adverse reaction, 76% had adverse reactions of mild severity. The proportion of subjects treated with ZEPATIER or placebo with serious adverse reactions was less than 1% in each treatment arm, and less than 1% and 3% of subjects, respectively, permanently discontinued treatment due to adverse reactions in each treatment arm.

Table 5: Adverse Reactions (All Intensity) Reported in ≥5% of Treatment-Naïve or PegIFN/RBV-Experienced Subjects with Stage 4 or 5 Chronic Kidney Disease and HCV Treated with ZEPATIER for 12 Weeks in C-SURFER
 | ZEPATIER N=122 % 12 weeks | Placebo N=113 % 12 weeks
Nausea | 11% | 8%
Headache | 11% | 5%
Fatigue | 5% | 8%

Laboratory Abnormalities in Subjects Receiving ZEPATIER with or without Ribavirin

Serum ALT Elevations

During clinical trials with ZEPATIER with or without ribavirin, regardless of treatment duration, 1% (12/1599) of subjects experienced elevations of ALT from normal levels to greater than 5 times the ULN, generally at or after treatment week 8 (mean onset time 10 weeks, range 6-12 weeks). These late ALT elevations were typically asymptomatic. Most late ALT elevations resolved with ongoing therapy with ZEPATIER or after completion of therapy [see Warnings and Precautions (5.2)]. The frequency of late ALT elevations was higher in subjects with higher grazoprevir plasma concentrations [see Drug Interactions (7.1) and Clinical Pharmacology (12.3)]. The incidence of late ALT elevations was not affected by treatment duration. Cirrhosis was not a risk factor for late ALT elevations.

Serum Bilirubin Elevations

During clinical trials with ZEPATIER with or without ribavirin, regardless of treatment duration, elevations in bilirubin at greater than 2.5 times ULN were observed in 6% of subjects receiving ZEPATIER with ribavirin compared to less than 1% in those receiving ZEPATIER alone. These bilirubin increases were predominately indirect and generally observed in association with ribavirin co-administration. Bilirubin elevations were typically not associated with serum ALT elevations.

Decreased Hemoglobin

During clinical trials with ZEPATIER with or without ribavirin, the mean change from baseline in hemoglobin levels in subjects treated with ZEPATIER for 12 weeks was –0.3 g per dL and with ZEPATIER with ribavirin for 16 weeks was approximately –2.2 g per dL. Hemoglobin declined during the first 8 weeks of treatment, remained low during the remainder of treatment, and normalized to baseline levels during follow-up. Less than 1% of subjects treated with ZEPATIER with ribavirin had hemoglobin levels decrease to less than 8.5 g per dL during treatment. No subjects treated with ZEPATIER alone had a hemoglobin level less than 8.5 g per dL.

Clinical Trial in Pediatric Subjects

Adverse Reactions in Pediatric Subjects 12 Years of Age and Older

The safety of ZEPATIER was assessed in pediatric subjects 12 years of age and older based on data from 22 subjects, without cirrhosis, who were treated with ZEPATIER for 12 weeks in a Phase 2b, open-label clinical trial (MK-5172-079). The adverse reactions observed were consistent with those observed in clinical trials of ZEPATIER in adults [see Clinical Studies (14.6)]. The adverse drug reactions observed in greater than or equal to 5% of subjects receiving ZEPATIER were headache (14%) and nausea (9%).

6.2 Postmarketing Experience

The following adverse reactions have been identified during post approval use of ZEPATIER. Because these reactions are reported voluntarily from a population of uncertain size, it is not always possible to reliably estimate their frequency or establish a causal relationship to drug exposure.

Skin and Subcutaneous Tissue Disorders

Angioedema

Hepatobiliary Disorders

Hepatic decompensation, hepatic failure [see Warnings and Precautions (5.3)]

7 DRUG INTERACTIONS

7.1 Potential for Drug Interactions

Grazoprevir is a substrate of OATP1B1/3 transporters. Co-administration of ZEPATIER with OATP1B1/3 inhibitors that are known or expected to significantly increase grazoprevir plasma concentrations is contraindicated [see Contraindications (4), Clinical Pharmacology (12.3), and Table 2].

Elbasvir and grazoprevir are substrates of CYP3A and P-gp, but the role of intestinal P-gp in the absorption of elbasvir and grazoprevir appears to be minimal. Co-administration of moderate or strong inducers of CYP3A with ZEPATIER may decrease elbasvir and grazoprevir plasma concentrations, leading to reduced therapeutic effect of ZEPATIER. Co-administration of ZEPATIER with strong CYP3A inducers or efavirenz is contraindicated [see Contraindications (4), Clinical Pharmacology (12.3), and Table 2]. Co-administration of ZEPATIER with moderate CYP3A inducers is not recommended [see Warnings and Precautions (5.5), Clinical Pharmacology (12.3), and Table 6]. Co-administration of ZEPATIER with strong CYP3A inhibitors may increase elbasvir and grazoprevir concentrations. Co-administration of ZEPATIER with certain strong CYP3A inhibitors is not recommended [see Warnings and Precautions (5.5), Clinical Pharmacology (12.3), and Table 6].

7.2 Established and other Potentially Significant Drug Interactions

If dose adjustments of concomitant medications are made due to treatment with ZEPATIER, doses should be readjusted after administration of ZEPATIER is completed.

Clearance of HCV infection with direct-acting antivirals may lead to changes in hepatic function, which may impact the safe and effective use of concomitant medications. For example, altered blood glucose control resulting in serious symptomatic hypoglycemia has been reported in diabetic patients in postmarketing case reports and published epidemiological studies. Management of hypoglycemia in these cases required either discontinuation or dose modification of concomitant medications used for diabetes treatment.

Frequent monitoring of relevant laboratory parameters (e.g., International Normalized Ratio [INR] in patients taking warfarin, blood glucose levels in diabetic patients) or drug concentrations of concomitant medications such as CYP450 substrates with a narrow therapeutic index (e.g., certain immunosuppressants) is recommended to ensure safe and effective use. Dose adjustments of concomitant medications may be necessary.

Table 6 provides a listing of established or potentially clinically significant drug interactions. The drug interactions described are based on studies conducted with either ZEPATIER, the components of ZEPATIER (elbasvir [EBR] and grazoprevir [GZR]) as individual agents, or are predicted drug interactions that may occur with ZEPATIER [see Contraindications (4), Warnings and Precautions (5.5), and Clinical Pharmacology (12.3)].

Table 6: Potentially Significant Drug Interactions: Alteration in Dose May Be Recommended Based on Results from Drug Interaction Studies or Predicted Interactions [This table is not all inclusive.]
Concomitant Drug Class: Drug Name | Effect on Concentration [↓ = decrease, ↑ = increase] | Clinical Comment
Antibiotics: Nafcillin | ↓ EBR ↓ GZR | Co-administration of ZEPATIER with nafcillin may lead to reduced therapeutic effect of ZEPATIER. Co-administration is not recommended.
Antifungals: oral Ketoconazole [These interactions have been studied in healthy adults.] | ↑ EBR ↑ GZR | Co-administration of oral ketoconazole is not recommended.
Endothelin Antagonists: Bosentan | ↓ EBR ↓ GZR | Co-administration of ZEPATIER with bosentan may lead to reduced therapeutic effect of ZEPATIER. Co-administration is not recommended.
Immunosuppressants: Tacrolimus | ↑ tacrolimus | Frequent monitoring of tacrolimus whole blood concentrations, changes in renal function, and tacrolimus-associated adverse events upon the initiation of co-administration is recommended.
HIV Medications:
Etravirine | ↓ EBR ↓ GZR | Co-administration of ZEPATIER with etravirine may lead to reduced therapeutic effect of ZEPATIER. Co-administration is not recommended.
Elvitegravir/ cobicistat/ emtricitabine/ tenofovir (disoproxil fumarate or alafenamide) | ↑ EBR ↑ GZR | Co-administration of cobicistat-containing regimens is not recommended.
HMG-CoA Reductase Inhibitors [See Drug Interactions (7.3) for a list of HMG Co-A reductase inhibitors without clinically relevant interactions with ZEPATIER.] :
Atorvastatin | ↑ atorvastatin | The dose of atorvastatin should not exceed a daily dose of 20 mg when co-administered with ZEPATIER.
Rosuvastatin | ↑ rosuvastatin | The dose of rosuvastatin should not exceed a daily dose of 10 mg when co-administered with ZEPATIER.
Fluvastatin Lovastatin Simvastatin | ↑ fluvastatin ↑ lovastatin ↑ simvastatin | Statin-associated adverse events such as myopathy should be closely monitored. The lowest necessary dose should be used when co-administered with ZEPATIER.
Wakefulness-Promoting Agents: Modafinil | ↓ EBR ↓ GZR | Co-administration of ZEPATIER with modafinil may lead to reduced therapeutic effect of ZEPATIER. Co-administration is not recommended.

7.3 Drugs without Clinically Significant Interactions with ZEPATIER

The interaction between the components of ZEPATIER (elbasvir or grazoprevir) or ZEPATIER and the following drugs were evaluated in clinical studies, and no dose adjustments are needed when ZEPATIER is used with the following drugs individually: acid reducing agents (proton pump inhibitors, H2 blockers, antacids), buprenorphine/naloxone, digoxin, dolutegravir, methadone, mycophenolate mofetil, oral contraceptive pills, phosphate binders, pitavastatin, pravastatin, prednisone, raltegravir, ribavirin, rilpivirine, tenofovir disoproxil fumarate, and sofosbuvir [see Clinical Pharmacology (12.3)].

No clinically relevant drug-drug interaction is expected when ZEPATIER is co-administered with abacavir, emtricitabine, entecavir, and lamivudine.

8 USE IN SPECIFIC POPULATIONS

8.1 Pregnancy

Risk Summary

No adequate human data are available to establish whether or not ZEPATIER poses a risk to pregnancy outcomes. In animal reproduction studies, no evidence of adverse developmental outcomes was observed with the components of ZEPATIER (elbasvir or grazoprevir) at exposures greater than those in humans at the recommended human dose (RHD) (see Data). During organogenesis in the rat and rabbit, systemic exposures (AUC) were approximately 10 and 18 times (for elbasvir) and 117 and 41 times (for grazoprevir), respectively, the exposure in humans at the RHD. In rat pre/postnatal developmental studies, maternal systemic exposures (AUC) to elbasvir and grazoprevir were approximately 10 and 78 times, respectively, the exposure in humans at the RHD.

The background risk of major birth defects and miscarriage for the indicated population is unknown. In the U.S. general population, the estimated background risk of major birth defects and miscarriage in clinically recognized pregnancies is 2-4% and 15-20%, respectively.

If ZEPATIER is administered with ribavirin, the combination regimen is contraindicated in pregnant women and in men whose female partners are pregnant. Refer to the ribavirin prescribing information for more information on use in pregnancy.

Data

Animal Data

Elbasvir: Elbasvir was administered orally at up to 1000 mg/kg/day to pregnant rats and rabbits on gestation days 6 to 20 and 7 to 20, respectively, and also to rats on gestation day 6 to lactation/post-partum day 20. No effects on embryo-fetal (rats and rabbits) or pre/postnatal (rats) development were observed at up to the highest dose tested. Systemic exposures (AUC) to elbasvir were approximately 10 (rats) and 18 (rabbits) times the exposure in humans at the RHD. In both species, elbasvir has been shown to cross the placenta, with fetal plasma concentrations of up to 0.8% (rabbits) and 2.2% (rats) that of maternal concentrations observed on gestation day 20.

Grazoprevir: Grazoprevir was administered to pregnant rats (oral doses up to 400 mg/kg/day) and rabbits (intravenous doses up to 100 mg/kg/day) on gestation days 6 to 20 and 7 to 20, respectively, and also to rats (oral doses up to 400 mg/kg/day) on gestation day 6 to lactation/post-partum day 20. No effects on embryo-fetal (rats and rabbits) or pre/postnatal (rats) development were observed at up to the highest dose tested. Systemic exposures (AUC) to grazoprevir were ≥78 (rats) and 41 (rabbits) times the exposure in humans at the RHD. In both species, grazoprevir has been shown to cross the placenta, with fetal plasma concentrations of up to 7% (rabbits) and 89% (rats) that of maternal concentrations observed on gestation day 20.

8.2 Lactation

Risk Summary

It is not known whether ZEPATIER is present in human breast milk, affects human milk production, or has effects on the breastfed infant. When administered to lactating rats, the components of ZEPATIER (elbasvir and grazoprevir) were present in milk, without effects on growth and development observed in nursing pups (see Data).

The developmental and health benefits of breastfeeding should be considered along with the mother's clinical need for ZEPATIER and any potential adverse effects on the breastfed child from ZEPATIER or from the underlying maternal condition.

If ZEPATIER is administered with ribavirin, the information for ribavirin with regard to nursing mothers also applies to this combination regimen. Refer to the ribavirin prescribing information for information on use during lactation.

Data

Elbasvir: No effects of elbasvir on growth and postnatal development were observed in nursing pups at up to the highest dose tested. Maternal systemic exposure (AUC) to elbasvir was approximately 10 times the exposure in humans at the RHD. Elbasvir was excreted into the milk of lactating rats following oral administration (1000 mg/kg/day) from gestation day 6 to lactation day 14, with milk concentrations approximately 4 times that of maternal plasma concentrations observed 2 hours post-dose on lactation day 14.

Grazoprevir: No effects of grazoprevir on growth and postnatal development were observed in nursing pups at up to the highest dose tested. Maternal systemic exposure (AUC) to grazoprevir was approximately 78 times the exposure in humans at the RHD. Grazoprevir was excreted into the milk of lactating rats following oral administration (up to 400 mg/kg/day) from gestation day 6 to lactation day 14, with milk concentrations of 54 and 87% that of maternal plasma concentrations observed 2 and 8 hours post-dose, respectively, on lactation day 14.

8.3 Females and Males of Reproductive Potential

If ZEPATIER is administered with ribavirin, the information for ribavirin with regard to pregnancy testing, contraception, and infertility also applies to this combination regimen. Refer to ribavirin prescribing information for additional information.

8.4 Pediatric Use

The safety, efficacy, and pharmacokinetics of ZEPATIER was evaluated in an open-label clinical trial (MK-5172-079), which included 22 subjects (n=21, genotype 1; n=1, genotype 4) 12 years of age and older who received ZEPATIER for 12 weeks. The safety, pharmacokinetics, and efficacy observed in this trial were comparable to those observed in adults [see Dosage and Administration (2.2), Adverse Reactions (6.1), Clinical Pharmacology (12.3), and Clinical Studies (14.6)].

Safety and effectiveness of ZEPATIER have not been established in pediatric patients younger than 12 years of age who weigh less than 30 kg.

8.5 Geriatric Use

Clinical trials of ZEPATIER with or without ribavirin included 187 subjects aged 65 years and over. Higher elbasvir and grazoprevir plasma concentrations were observed in subjects aged 65 years and over. A higher rate of late ALT elevations was observed in subjects aged 65 years and over in clinical trials [see Warnings and Precautions (5.2)]. However, no dosage adjustment of ZEPATIER is recommended in geriatric patients [see Clinical Pharmacology (12.3)].

8.6 Gender

Higher elbasvir and grazoprevir plasma concentrations were observed in females compared to males. Females experienced a higher rate of late ALT elevations in clinical trials [see Warnings and Precautions (5.2)]. However, no dose adjustment of ZEPATIER is recommended based on gender [see Clinical Pharmacology (12.3)].

8.7 Race

Higher elbasvir and grazoprevir plasma concentrations were observed in Asians compared to Caucasians. Asians experienced a higher rate of late ALT elevations in clinical trials [see Warnings and Precautions (5.2)]. However, no dose adjustment of ZEPATIER is recommended based on race/ethnicity [see Clinical Pharmacology (12.3)].

8.8 Renal Impairment

No dosage adjustment of ZEPATIER is recommended in patients with any degree of renal impairment including patients receiving hemodialysis [see Clinical Pharmacology (12.3)]. Administer ZEPATIER with or without ribavirin according to recommendations in Table 1 [see Dosage and Administration (2.2, 2.3)]. Refer to the prescribing information for ribavirin tablets for renal dosage adjustment of ribavirin in patients with CrCl less than or equal to 50 mL per minute.

8.9 Hepatic Impairment

No dosage adjustment of ZEPATIER is recommended in patients with mild hepatic impairment (Child-Pugh A). ZEPATIER is contraindicated in patients with moderate hepatic impairment (Child-Pugh B) due to the lack of clinical safety and efficacy experience in HCV-infected Child-Pugh B patients, and in patients with severe hepatic impairment (Child-Pugh C) due to a 12-fold increase in grazoprevir exposure in non-HCV infected Child-Pugh C subjects. In addition, postmarketing cases of hepatic decompensation/failure have been reported in patients with advanced liver disease [see Dosage and Administration (2.4), Contraindications (4), Warnings and Precautions (5.3), and Clinical Pharmacology (12.3)].

The safety and efficacy of ZEPATIER have not been established in patients awaiting liver transplant or in liver transplant recipients.

10 OVERDOSAGE

Human experience of overdose with ZEPATIER is limited. No specific antidote is available for overdose with ZEPATIER. In case of overdose, it is recommended that the patient be monitored for any signs or symptoms of adverse reactions and appropriate symptomatic treatment instituted.

Hemodialysis does not remove elbasvir or grazoprevir since elbasvir and grazoprevir are highly bound to plasma protein [see Clinical Pharmacology (12.3)].

11 DESCRIPTION

ZEPATIER is a fixed-dose combination tablet containing elbasvir and grazoprevir for oral administration.

Elbasvir is an HCV NS5A inhibitor, and grazoprevir is an HCV NS3/4A protease inhibitor.

Each tablet contains 50 mg elbasvir and 100 mg grazoprevir. The tablets include the following inactive ingredients: colloidal silicon dioxide, copovidone, croscarmellose sodium, hypromellose, lactose monohydrate, magnesium stearate, mannitol, microcrystalline cellulose, sodium chloride, sodium lauryl sulfate, and vitamin E polyethylene glycol succinate. The tablets are film-coated with a coating material containing the following inactive ingredients: carnauba wax, ferrosoferric oxide, hypromellose, iron oxide red, iron oxide yellow, lactose monohydrate, titanium dioxide, and triacetin.

Elbasvir:

The IUPAC name for elbasvir is Dimethyl N,N'-([(6S)-6-phenylindolo[1,2-c][1,3]benzoxazine-3,10-diyl]bis{1H-imidazole-5,2-diyl-(2S)-pyrrolidine-2,1-diyl[(2S)-3-methyl-1-oxobutane-1,2-diyl]})dicarbamate.

It has a molecular formula of C49H55N9O7 and a molecular weight of 882.02. It has the following structural formula:

Elbasvir is practically insoluble in water (less than 0.1 mg per mL) and very slightly soluble in ethanol (0.2 mg per mL), but is very soluble in ethyl acetate and acetone.

Grazoprevir:

The IUPAC name for grazoprevir is (1aR,5S,8S,10R,22aR)-N-[(1R,2S)-1-[(Cyclopropylsulfonamido)carbonyl]-2-ethenylcyclopropyl]-14-methoxy-5-(2-methylpropan-2-yl)-3,6-dioxo-1,1a,3,4,5,6,9,10,18,19,20,21,22,22a-tetradecahydro-8H-7,10-methanocyclopropa[18,19][1,10,3,6]dioxadiazacyclononadecino[11,12-b]quinoxaline-8-carboxamide.

It has a molecular formula of C38H50N6O9S and a molecular weight of 766.90. It has the following structural formula:

Grazoprevir is practically insoluble in water (less than 0.1 mg per mL) but is freely soluble in ethanol and some organic solvents (e.g., acetone, tetrahydrofuran and N,N-dimethylformamide).

12 CLINICAL PHARMACOLOGY

12.1 Mechanism of Action

ZEPATIER is a fixed-dose combination of elbasvir and grazoprevir which are direct-acting antiviral agents against the hepatitis C virus [see Microbiology (12.4)].

12.2 Pharmacodynamics

Cardiac Electrophysiology

Thorough QT studies have been conducted for elbasvir and grazoprevir.

The effect of elbasvir 700 mg on QTc interval was evaluated in a randomized, single-dose, placebo- and active-controlled (moxifloxacin 400 mg) 3-period crossover thorough QT trial in 42 healthy subjects. At a concentration 3 to 4 times the therapeutic concentration, elbasvir does not prolong QTc to any clinically relevant extent.

The effect of grazoprevir 1600 mg (16 times the approved dose) on QTc interval was evaluated in a randomized, single-dose, placebo- and active-controlled (moxifloxacin 400 mg) 3-period crossover thorough QT trial in 41 healthy subjects. At a concentration 40 times the therapeutic concentration, grazoprevir does not prolong QTc to any clinically relevant extent.

12.3 Pharmacokinetics

The pharmacokinetic properties of elbasvir and grazoprevir have been evaluated in non-HCV-infected adult subjects and in HCV-infected adult subjects. Elbasvir pharmacokinetics were similar in healthy subjects and HCV-infected subjects and were approximately dose-proportional over the range of 5-100 mg once daily. Grazoprevir oral exposures are approximately 2-fold greater in HCV-infected subjects as compared to healthy subjects. Grazoprevir pharmacokinetics increased in a greater than dose-proportional manner over the range of 10-800 mg once daily in HCV-infected subjects. Ribavirin co-administration with ZEPATIER had no clinically relevant impact on plasma AUC and Cmax of elbasvir and grazoprevir compared to administration of ZEPATIER alone. The geometric mean steady-state pharmacokinetic parameter values for elbasvir and grazoprevir in non-cirrhotic HCV-infected subjects are provided in Table 7. Following once daily administration of ZEPATIER to HCV-infected subjects, elbasvir and grazoprevir reached steady state within approximately 6 days.

Table 7: Geometric Mean (90% Confidence Interval) for Elbasvir and Grazoprevir Steady State Pharmacokinetic Parameter Values in Non-Cirrhotic HCV-Infected Subjects Estimated Based on Population Pharmacokinetic Modeling
 | Geometric Mean (90% Confidence Interval)
 | AUC0-24 (ng•hr/mL) | Cmax (ng/mL) | C24 (ng/mL)
Elbasvir | 1920 (1880, 1960) | 121 (118, 123) | 48.4 (47.3, 49.6)
Grazoprevir | 1420 (1400, 1530) | 165 (161, 176) | 18.0 (17.8, 19.9)

Absorption

Following administration of ZEPATIER to HCV-infected subjects, elbasvir peak concentrations occur at a median Tmax of 3 hours (range of 3 to 6 hours); grazoprevir peak concentrations occur at a median Tmax of 2 hours (range of 30 minutes to 3 hours). The absolute bioavailability of elbasvir is estimated to be 32%, and grazoprevir is estimated to be 27%.

Effect of Food

Relative to fasting conditions, the administration of a single dose of ZEPATIER with a high-fat (900 kcal, 500 kcal from fat) meal to healthy subjects resulted in decreases in elbasvir AUC0-inf and Cmax of approximately 11% and 15%, respectively, and increases in grazoprevir AUC0-inf and Cmax of approximately 1.5-fold and 2.8-fold, respectively. These differences in elbasvir and grazoprevir exposure are not clinically relevant; therefore, ZEPATIER may be taken without regard to food [see Dosage and Administration (2.2)].

Distribution

Elbasvir and grazoprevir are extensively bound (greater than 99.9% and 98.8%, respectively) to human plasma proteins. Both elbasvir and grazoprevir bind to human serum albumin and α1-acid glycoprotein. Estimated apparent volume of distribution values of elbasvir and grazoprevir are approximately 680 L and 1250 L, respectively, based on population pharmacokinetic modeling.

In preclinical distribution studies, elbasvir distributes into most tissues including the liver; whereas grazoprevir distributes predominantly to the liver likely facilitated by the active transport through the OATP1B1/3 liver uptake transporter.

Elimination

The geometric mean apparent terminal half-life for elbasvir (50 mg) and grazoprevir (100 mg) is approximately 24 and 31 hours, respectively, in HCV-infected subjects.

Metabolism

Elbasvir and grazoprevir are partially eliminated by oxidative metabolism, primarily by CYP3A. No circulating metabolites of either elbasvir or grazoprevir were detected in human plasma.

Excretion

The primary route of elimination of elbasvir and grazoprevir is through feces with almost all (greater than 90%) of radiolabeled dose recovered in feces compared to less than 1% in urine.

Specific Populations

Pediatric Population

The pharmacokinetics of elbasvir and grazoprevir were evaluated in 22 pediatric subjects 12 years of age and older, with HCV genotype 1 or 4, who received a daily dose of ZEPATIER (50 mg elbasvir/100 mg grazoprevir). The pharmacokinetic properties of elbasvir and grazoprevir in pediatric subjects 12 years of age and older are provided in Table 8. Exposures in pediatric subjects were comparable to those observed in adults.

Table 8: Geometric Mean (90% Confidence Interval) for Elbasvir and Grazoprevir Steady State Pharmacokinetic Parameter Values in Non-Cirrhotic HCV-Infected Pediatric Subjects Ages 12 to <18 Years
PK Parameters [AUC0-24 and Cmax N=22; Ctrough N=21] | Geometric Mean (90% Confidence Interval)
PK Parameters [AUC0-24 and Cmax N=22; Ctrough N=21] | AUC0-24 (ng•hr/mL) | Cmax (ng/mL) | C24 (ng/mL)
Elbasvir | 2120 (1800, 2510) | 167 (140, 199) | 50.3 (41.7, 60.6)
Grazoprevir | 1110 (871, 1410) | 188 (140, 253) | 11.7 (9.43, 14.5)

Geriatric Population

In population pharmacokinetic analyses, elbasvir and grazoprevir AUCs are estimated to be 16% and 45% higher, respectively, in subjects at least 65 years of age compared to subjects less than 65 years of age.

Gender

In population pharmacokinetic analyses, elbasvir and grazoprevir AUCs are estimated to be 50% and 30% higher, respectively, in females compared to males.

Weight/BMI

In population pharmacokinetic analyses, there was no effect of weight on elbasvir pharmacokinetics. Grazoprevir AUC is estimated to be 15% higher in a 53 kg subject compared to a 77 kg subject. This change is not clinically relevant for grazoprevir.

Race/Ethnicity

In population pharmacokinetic analyses, elbasvir and grazoprevir AUCs are estimated to be 15% and 50% higher, respectively, for Asians compared to Caucasians. Population pharmacokinetics estimates of exposure of elbasvir and grazoprevir were comparable between Caucasians and Black/African Americans.

Renal Impairment

In population pharmacokinetic analyses, elbasvir AUC was 25% higher in hemodialysis-dependent subjects and 46% higher in non-dialysis-dependent subjects with severe renal impairment compared to elbasvir AUC in subjects without severe renal impairment. In population pharmacokinetic analysis in HCV-infected subjects, grazoprevir AUC was 10% higher in hemodialysis-dependent subjects and 40% higher in non-dialysis-dependent subjects with severe renal impairment compared to grazoprevir AUC in subjects without severe renal impairment. Elbasvir and grazoprevir are not removed by hemodialysis. Elbasvir and grazoprevir are unlikely to be removed by peritoneal dialysis as both are highly protein bound.

Overall, changes in exposure of elbasvir and grazoprevir in HCV-infected subjects with renal impairment with or without hemodialysis are not clinically relevant [see Use in Specific Populations (8.8)].

Hepatic Impairment

The pharmacokinetics of elbasvir and grazoprevir were evaluated in non-HCV-infected subjects with mild hepatic impairment (Child-Pugh Category A [CP-A], score of 5-6), moderate hepatic impairment (Child-Pugh Category B [CP-B], score of 7-9) and severe hepatic impairment (Child-Pugh Category C [CP-C], score of 10-15). In addition, the pharmacokinetics of elbasvir and grazoprevir were also evaluated in HCV-infected subjects including CP-A subjects with compensated cirrhosis.

Relative to non-HCV-infected subjects with normal hepatic function, no clinically relevant differences in elbasvir AUC values were observed in non-HCV-infected subjects with mild, moderate, or severe hepatic impairment. In population pharmacokinetic analyses, elbasvir steady-state AUC was similar in HCV-infected subjects with compensated cirrhosis compared to HCV-infected, non-cirrhotic subjects.

Relative to non-HCV-infected subjects with normal hepatic function, grazoprevir AUC values were higher by 1.7-fold, 5-fold, and 12-fold in non-HCV-infected subjects with mild, moderate, and severe hepatic impairment, respectively. In population pharmacokinetic analyses, grazoprevir steady-state AUC values were higher by 1.65-fold in HCV-infected subjects with compensated cirrhosis compared to HCV-infected, non-cirrhotic subjects.

Drug Interaction Studies

Drug interaction studies were performed in healthy adults with elbasvir, grazoprevir, or co-administered elbasvir and grazoprevir and drugs likely to be co-administered or drugs commonly used as probes for pharmacokinetic interactions. Table 9 summarizes the effects of co-administered drugs on the exposures of the individual components of ZEPATIER (elbasvir and grazoprevir). Table 10 summarizes the effects of the individual components of ZEPATIER on the exposures of the co-administered drugs. For information regarding clinical recommendations, [see Contraindications (4), Warnings and Precautions (5), and Drug Interactions (7)].

Elbasvir and grazoprevir are substrates of CYP3A and P-gp, but the role of intestinal P-gp in the absorption of elbasvir and grazoprevir appears to be minimal. Co-administration of moderate and strong CYP3A inducers with ZEPATIER may decrease elbasvir and grazoprevir plasma concentrations, leading to reduced therapeutic effect of ZEPATIER. Co-administration of strong CYP3A4 inhibitors with ZEPATIER may increase elbasvir and grazoprevir plasma concentrations.

Grazoprevir is a substrate of OATP1B1/3. Co-administration of ZEPATIER with drugs that inhibit OATP1B1/3 transporters may result in a clinically relevant increase in grazoprevir plasma concentrations.

Elbasvir is not a CYP3A inhibitor in vitro and grazoprevir is a weak CYP3A inhibitor in humans. Co-administration with grazoprevir resulted in a 34% increase in plasma exposure of midazolam and a 43% increase in plasma exposure of tacrolimus (see Tables 6 and 10). Elbasvir inhibited P-gp in vitro, but no clinically relevant increases in concentrations of digoxin (a P-gp substrate; see Table 10) were observed by co-administration of elbasvir. Grazoprevir is not a P-gp inhibitor in vitro. Elbasvir and grazoprevir are inhibitors of the drug transporter breast cancer resistance protein (BCRP) at the intestinal level in humans and may increase plasma concentrations of co-administered BCRP substrates.

Clinically significant drug interactions with ZEPATIER as an inhibitor of other CYP enzymes (CYP1A2, CYP2B6, CYP2C8, CYP2C9, CYP2C19, and CYP2D6), UGT1A1, esterases (CES1, CES2, and CatA), organic anion transporters (OAT)1 and OAT3, and organic cation transporter (OCT)2, are not expected, and multiple-dose administration of elbasvir or grazoprevir is unlikely to induce the metabolism of drugs metabolized by CYP1A2, CYP2B6, or CYP3A based on in vitro data.

Table 9: Drug Interactions: Changes in Pharmacokinetics of Elbasvir or Grazoprevir in the Presence of Co-Administered Drug
Co-Administered Drug | Regimen of Co-Administered Drug | Regimen of EBR or/and GZR | N | Geometric Mean Ratio [90% CI] of EBR and GZR PK with/without Co-Administered Drug (No Effect=1.00)
Co-Administered Drug | Regimen of Co-Administered Drug | Regimen of EBR or/and GZR | N |  | AUC [AUC0-inf for single-dose, AUC0-24 for once daily.] | Cmax | C24
Antifungal
Ketoconazole | 400 mg once daily | EBR 50 mg single-dose | 7 | EBR | 1.80 (1.41, 2.29) | 1.29 (1.00, 1.66) | 1.89 (1.37, 2.60)
Ketoconazole | 400 mg once daily | GZR 100 mg single-dose | 8 | GZR | 3.02 (2.42, 3.76) | 1.13 (0.77, 1.67) | 2.01 (1.49, 2.71)
Antimycobacterial
Rifampin | 600 mg single-dose IV | EBR 50 mg single-dose | 14 | EBR | 1.22 (1.06, 1.40) | 1.41 (1.18, 1.68) | 1.31 (1.12, 1.53)
Rifampin | 600 mg single-dose PO | EBR 50 mg single-dose | 14 | EBR | 1.17 (0.98, 1.39) | 1.29 (1.06, 1.58) | 1.21 (1.03, 1.43)
Rifampin | 600 mg PO once daily | GZR 200 mg once daily | 12 | GZR | 0.93 (0.75, 1.17) | 1.16 (0.82, 1.65) | 0.10 (0.07, 0.13)
Rifampin | 600 mg IV single-dose | GZR 200 mg single-dose | 12 | GZR | 10.21 (8.68, 12.00) | 10.94 (8.92, 13.43) | 1.77 (1.40, 2.24)
Rifampin | 600 mg PO single-dose | GZR 200 mg once daily | 12 | GZR | 8.35 (7.38, 9.45) [AUC0-24] | 6.52 (5.16, 8.24) | 1.62 (1.32, 1.98)
HCV Antiviral
EBR | 20 mg once daily | GZR 200 mg once daily | 10 | GZR | 0.90 (0.63, 1.28) | 0.87 (0.50, 1.52) | 0.94 (0.77, 1.15)
GZR | 200 mg once daily | EBR 20 mg once daily | 10 | EBR | 1.01 (0.83, 1.24) | 0.93 (0.76, 1.13) | 1.02 (0.83, 1.24)
HIV Protease Inhibitor
Atazanavir/ ritonavir | 300 mg/100 mg once daily | EBR 50 mg once daily | 10 | EBR | 4.76 (4.07, 5.56) | 4.15 (3.46, 4.97) | 6.45 (5.51, 7.54)
Atazanavir/ ritonavir | 300 mg/100 mg once daily | GZR 200 mg once daily | 12 | GZR | 10.58 (7.78, 14.39) | 6.24 (4.42, 8.81) | 11.64 (7.96, 17.02)
Darunavir/ ritonavir | 600 mg/100 mg twice daily | EBR 50 mg once daily | 10 | EBR | 1.66 (1.35, 2.05) | 1.67 (1.36, 2.05) | 1.82 (1.39, 2.39)
Darunavir/ ritonavir | 600 mg/100 mg twice daily | GZR 200 mg once daily | 13 | GZR | 7.50 (5.92, 9.51) | 5.27 (4.04, 6.86) | 8.05 (6.33, 10.24)
Lopinavir/ ritonavir | 400 mg/100 mg twice daily | EBR 50 mg once daily | 10 | EBR | 3.71 (3.05, 4.53) | 2.87 (2.29, 3.58) | 4.58 (3.72, 5.64)
Lopinavir/ ritonavir | 400 mg/100 mg twice daily | GZR 200 mg once daily | 13 | GZR | 12.86 (10.25, 16.13) | 7.31 (5.65, 9.45) | 21.70 (12.99, 36.25)
Ritonavir [Higher doses of ritonavir have not been tested in a drug interaction study with GZR.] | 100 mg twice daily | GZR 200 mg single-dose | 10 | GZR | 2.03 (1.60, 2.56) | 1.15 (0.60, 2.18) | 1.88 (1.65, 2.14)
HIV Integrase Strand Transfer Inhibitor
Dolutegravir | 50 mg single-dose | EBR 50 mg + GZR 200 mg once daily | 12 | EBR | 0.98 (0.93, 1.04) | 0.97 (0.89, 1.05) | 0.98 (0.93, 1.03)
Dolutegravir | 50 mg single-dose | EBR 50 mg + GZR 200 mg once daily | 12 | GZR | 0.81 (0.67, 0.97) | 0.64 (0.44, 0.93) | 0.86 (0.79, 0.93)
Raltegravir | 400 mg single-dose | EBR 50 mg single-dose | 10 | EBR | 0.81 (0.57, 1.17) | 0.89 (0.61, 1.29) | 0.80 (0.55, 1.16)
Raltegravir | 400 mg twice daily | GZR 200 mg once daily | 11 | GZR | 0.89 (0.72, 1.09) | 0.85 (0.62, 1.16) | 0.90 (0.82, 0.99)
HIV Non-Nucleoside Reverse Transcriptase Inhibitor
Efavirenz | 600 mg once daily | EBR 50 mg once daily | 10 | EBR | 0.46 (0.36, 0.59) | 0.55 (0.41, 0.73) | 0.41 (0.28, 0.59)
Efavirenz | 600 mg once daily | GZR 200 mg once daily | 12 | GZR | 0.17 (0.13, 0.24) | 0.13 (0.09, 0.19) | 0.31 (0.25, 0.38)
Rilpivirine | 25 mg once daily | EBR 50 mg + GZR 200 mg once daily | 19 | EBR | 1.07 (1.00, 1.15) | 1.07 (0.99, 1.16) | 1.04 (0.98, 1.11)
Rilpivirine | 25 mg once daily | EBR 50 mg + GZR 200 mg once daily | 19 | GZR | 0.98 (0.89, 1.07) | 0.97 (0.83, 1.14) | 1.00 (0.93, 1.07)
HIV Nucleotide Reverse Transcriptase Inhibitor
Tenofovir disoproxil fumarate | 300 mg once daily | EBR 50 mg once daily | 10 | EBR | 0.93 (0.82, 1.05) | 0.88 (0.77, 1.00) | 0.92 (0.81, 1.05)
Tenofovir disoproxil fumarate | 300 mg once daily | GZR 200 mg once daily | 12 | GZR | 0.86 (0.65, 1.12) | 0.78 (0.51, 1.18) | 0.89 (0.78, 1.01)
HIV Fixed-Dose Combination Regimen
Elvitegravir/ cobicistat/ emtricitabine/ tenofovir disoproxil fumarate | 150 mg/ 150 mg/ 200 mg/ 300 mg once daily | EBR 50 mg/ GZR 100 mg once daily | 21 | EBR | 2.18 (2.02, 2.35) | 1.91 (1.77, 2.05) | 2.38 (2.19, 2.60)
Elvitegravir/ cobicistat/ emtricitabine/ tenofovir disoproxil fumarate | 150 mg/ 150 mg/ 200 mg/ 300 mg once daily | EBR 50 mg/ GZR 100 mg once daily | 21 | GZR | 5.36 (4.48, 6.43) | 4.59 (3.70, 5.69) | 2.78 (2.48, 3.11)
Immunosuppressant
Cyclosporine | 400 mg single-dose | EBR 50 mg + GZR 200 mg once daily | 14 | EBR | 1.98 (1.84, 2.13) | 1.95 (1.84, 2.07) | 2.21 (1.98, 2.47)
Cyclosporine | 400 mg single-dose | EBR 50 mg + GZR 200 mg once daily | 14 | GZR | 15.21 (12.83, 18.04) | 17.00 (12.94, 22.34) | 3.39 (2.82, 4.09)
Mycophenolate mofetil | 1000 mg single-dose | EBR 50 mg + GZR 200 mg once daily | 14 | EBR | 1.07 (1.00, 1.14) | 1.07 (0.98, 1.16) | 1.05 (0.97, 1.14)
Mycophenolate mofetil | 1000 mg single-dose | EBR 50 mg + GZR 200 mg once daily | 14 | GZR | 0.74 (0.60, 0.92) | 0.58 (0.42, 0.82) | 0.97 (0.89, 1.06)
Prednisone | 40 mg single-dose | EBR 50 mg + GZR 200 mg once daily | 14 | EBR | 1.17 (1.11, 1.24) | 1.25 (1.16, 1.35) | 1.04 (0.97, 1.12)
Prednisone | 40 mg single-dose | EBR 50 mg + GZR 200 mg once daily | 14 | GZR | 1.09 (0.95, 1.25) | 1.34 (1.10, 1.62) | 0.93 (0.87, 1.00)
Tacrolimus | 2 mg single-dose | EBR 50 mg + GZR 200 mg once daily | 16 | EBR | 0.97 (0.90, 1.06) | 0.99 (0.88, 1.10) | 0.92 (0.83, 1.02)
Tacrolimus | 2 mg single-dose | EBR 50 mg + GZR 200 mg once daily | 16 | GZR | 1.12 (0.97, 1.30) | 1.07 (0.83, 1.37) | 0.94 (0.87, 1.02)
Opioid-Substitution Therapy
Buprenorphine/naloxone | 8 mg/2 mg single-dose | EBR 50 mg single-dose | 15 | EBR | 1.22 (0.98, 1.52) | 1.13 (0.87, 1.46) | 1.22 (0.99, 1.51)
Buprenorphine/naloxone | 8-24 mg/ 2-6 mg once daily | GZR 200 mg once daily | 12 [The reference (EBR or GZR alone) for the analysis consisted of subjects pooled across Phase I studies.] | GZR | 0.86 (0.63, 1.18) | 0.80 (0.54, 1.20) | 0.97 (0.77, 1.22)
Methadone | 20-120 mg once daily | EBR 50 mg once daily | 10 | EBR | 1.20 (0.94, 1.53) | 1.23 (0.94, 1.62) | 1.32 (1.03, 1.68)
Methadone | 20-150 mg once daily | GZR 200 mg once daily | 12 | GZR | 1.03 (0.76, 1.41) | 0.89 (0.60, 1.32) | 0.98 (0.79, 1.23)
Acid-Reducing Agent
Famotidine | 20 mg single-dose | EBR 50 mg/ GZR 100 mg single-dose | 16 | EBR | 1.05 (0.92, 1.18) | 1.11 (0.98, 1.26) | 1.03 (0.91, 1.17)
Famotidine | 20 mg single-dose | EBR 50 mg/ GZR 100 mg single-dose | 16 | GZR | 1.10 (0.95, 1.28) | 0.89 (0.71, 1.11) | 1.12 (0.97, 1.30)
Pantoprazole | 40 mg once daily | EBR 50 mg/ GZR 100 mg single-dose | 16 | EBR | 1.05 (0.93, 1.18) | 1.02 (0.92, 1.14) | 1.03 (0.92, 1.17)
Pantoprazole | 40 mg once daily | EBR 50 mg/ GZR 100 mg single-dose | 16 | GZR | 1.12 (0.96, 1.30) | 1.10 (0.89, 1.37) | 1.17 (1.02, 1.34)
Phosphate Binder
Calcium acetate | 2668 mg single-dose | EBR 50 mg + GZR 100 mg single-dose | 12 | EBR | 0.92 (0.75, 1.14) | 0.86 (0.71, 1.04) | 0.87 (0.70, 1.09)
Calcium acetate | 2668 mg single-dose | EBR 50 mg + GZR 100 mg single-dose | 12 | GZR | 0.79 (0.68, 0.91) | 0.57 (0.40, 0.83) | 0.77 (0.61, 0.99)
Sevelamer carbonate | 2400 mg single-dose | EBR 50 mg + GZR 100 mg single-dose | 12 | EBR | 1.13 (0.94, 1.37) | 1.07 (0.88, 1.29) | 1.22 (1.02, 1.45)
Sevelamer carbonate | 2400 mg single-dose | EBR 50 mg + GZR 100 mg single-dose | 12 | GZR | 0.82 (0.68, 0.99) | 0.53 (0.37, 0.76) | 0.84 (0.71, 0.99)
Statin
Atorvastatin | 20 mg single-dose | GZR 200 mg once daily | 9 | GZR | 1.26 (0.97, 1.64) | 1.26 (0.83, 1.90) | 1.11 (1.00, 1.23)
Pitavastatin | 1 mg single-dose | GZR 200 mg once daily | 9 | GZR | 0.81 (0.70, 0.95) | 0.72 (0.57, 0.92) | 0.91 (0.82, 1.01)
Pravastatin | 40 mg single-dose | EBR 50 mg + GZR 200 mg once daily | 12 | EBR | 0.98 (0.93, 1.02) | 0.97 (0.89, 1.05) | 0.97 (0.92, 1.02)
Pravastatin | 40 mg single-dose | EBR 50 mg + GZR 200 mg once daily | 12 | GZR | 1.24 (1.00, 1.53) | 1.42 (1.00, 2.03) | 1.07 (0.99, 1.16)
Rosuvastatin | 10 mg single-dose | EBR 50 mg + GZR 200 mg single-dose | 11 | EBR | 1.09 (0.98, 1.21) | 1.11 (0.99, 1.26) | 0.96 (0.86, 1.08)
Rosuvastatin | 10 mg single-dose | GZR 200 mg once daily | 11 | GZR | 1.16 (0.94, 1.44) | 1.13 (0.77, 1.65) | 0.93 (0.84, 1.03)
Rosuvastatin | 10 mg single-dose | EBR 50 mg + GZR 200 mg once daily | 11 | GZR | 1.01 (0.79, 1.28) | 0.97 (0.63, 1.50) | 0.95 (0.87, 1.04)
Abbreviations: EBR, elbasvir; GZR, grazoprevir; IV, intravenous; PO, oral; EBR + GZR, administration of EBR and GZR as separate pills; EBR/GZR, administration of EBR and GZR as a single fixed-dose combination tablet.

Table 10: Drug Interactions: Changes in Pharmacokinetics for Co-Administered Drug in the Presence of Elbasvir, Grazoprevir, or Co-Administered Elbasvir and Grazoprevir
Co-Administered Drug | Regimen of Co-Administered Drug | EBR or/and GZR Administration | EBR or/and GZR Regimen | N | Geometric Mean Ratio [90% CI] of Co-Administered Drug PK with/without EBR or/and GZR (No Effect=1.00)
Co-Administered Drug | Regimen of Co-Administered Drug | EBR or/and GZR Administration | EBR or/and GZR Regimen | N | AUC [AUC0-inf for single-dose administration; AUC0-24 for once daily administration; AUC0-12 for twice daily administration] | Cmax | Ctrough [C24 for once daily administration; C12 for twice daily administration.]
P-gp Substrate
Digoxin | Digoxin 0.25 mg single-dose | EBR | 50 mg once daily | 18 | 1.11 (1.02, 1.22) | 1.47 (1.25, 1.73) | --
CYP3A Substrate
Midazolam | Midazolam 2 mg single-dose | GZR | 200 mg once daily | 11 | 1.34 (1.29, 1.39) | 1.15 (1.01, 1.31) | --
CYP2C8 Substrate
Montelukast | Montelukast 10 mg single-dose | GZR | 200 mg once daily | 23 | 1.11 (1.01, 1.20) | 0.92 (0.81, 1.06) | 1.39 (1.25, 1.56)
HCV Antiviral
GS-331007 | Sofosbuvir 400 mg single-dose | EBR + GZR | 50 mg + 200 mg once daily | 16 | 1.13 (1.05, 1.21) | 0.87 (0.78, 0.96) | 1.53 (1.43, 1.63)
Sofosbuvir | Sofosbuvir 400 mg single-dose | EBR + GZR | 50 mg + 200 mg once daily | 16 | 2.43 (2.12, 2.79) [N=14] | 2.27 (1.72, 2.99) | --
HIV Protease Inhibitor
Atazanavir/ ritonavir | Atazanavir 300 mg/ ritonavir 100 mg once daily | EBR | 50 mg once daily | 8 | 1.07 (0.98, 1.17) | 1.02 (0.96, 1.08) | 1.15 (1.02, 1.29)
Atazanavir/ ritonavir | Atazanavir 300 mg/ ritonavir 100 mg once daily | GZR | 200 mg once daily | 11 | 1.43 (1.30, 1.57) | 1.12 (1.01, 1.24) | 1.23 (1.13, 1.34)
Darunavir/ ritonavir | Darunavir 600 mg/ ritonavir 100 mg twice daily | EBR | 50 mg once daily | 8 | 0.95 (0.86, 1.06) | 0.95 (0.85, 1.05) | 0.94 (0.85, 1.05)
Darunavir/ ritonavir | Darunavir 600 mg/ ritonavir 100 mg twice daily | GZR | 200 mg once daily | 13 | 1.11 (0.99, 1.24) | 1.10 (0.96, 1.25) | 1.00 (0.85, 1.18)
Lopinavir/ ritonavir | Lopinavir 400 mg/ ritonavir 100 mg twice daily | EBR | 50 mg once daily | 9 | 1.02 (0.93, 1.13) | 1.02 (0.92, 1.13) | 1.07 (0.97, 1.18)
Lopinavir/ ritonavir | Lopinavir 400 mg/ ritonavir 100 mg twice daily | GZR | 200 mg once daily | 13 | 1.03 (0.96, 1.16) | 0.97 (0.88, 1.08) | 0.97 (0.81, 1.15)
HIV Integrase Strand Transfer Inhibitor
Dolutegravir | Dolutegravir 50 mg single-dose | EBR + GZR | 50 mg + 200 mg once daily | 12 | 1.16 (1.00, 1.34) | 1.22 (1.05, 1.40) | 1.14 (0.95, 1.36)
Raltegravir | Raltegravir 400 mg single-dose | EBR | 50 mg single-dose | 10 | 1.02 (0.81, 1.27) | 1.09 (0.83, 1.44) | 0.99 (0.80, 1.22) [C12]
Raltegravir | Raltegravir 400 mg twice daily | GZR | 200 mg once daily | 11 | 1.43 (0.89, 2.30) | 1.46 (0.78, 2.73) | 1.47 (1.09, 2.00)
HIV Non-Nucleoside Reverse Transcriptase Inhibitor
Efavirenz | Efavirenz 600 mg once daily | EBR | 50 mg once daily | 7 | 0.82 (0.78, 0.86) | 0.74 (0.67, 0.82) | 0.91 (0.87, 0.96)
Efavirenz | Efavirenz 600 mg once daily | GZR | 200 mg once daily | 11 | 1.00 (0.96, 1.05) | 1.03 (0.99, 1.08) | 0.93 (0.88, 0.98)
Rilpivirine | Rilpivirine 25 mg once daily | EBR + GZR | 50 mg + 200 mg once daily | 19 | 1.13 (1.07, 1.20) | 1.07 (0.97, 1.17) | 1.16 (1.09, 1.23)
HIV Nucleotide Reverse Transcriptase Inhibitor
Tenofovir disoproxil fumarate | Tenofovir disoproxil fumarate 300 mg once daily | EBR | 50 mg once daily | 10 | 1.34 (1.23, 1.47) | 1.47 (1.32, 1.63) | 1.29 (1.18, 1.41)
Tenofovir disoproxil fumarate | Tenofovir disoproxil fumarate 300 mg once daily | GZR | 200 mg once daily | 12 | 1.18 (1.09, 1.28) | 1.14 (1.04, 1.25) | 1.24 (1.10, 1.39)
Tenofovir disoproxil fumarate | Tenofovir disoproxil fumarate 300 mg once daily | EBR/GZR | 50 mg + 100 mg once daily | 13 | 1.27 (1.20, 1.35) | 1.14 (0.95, 1.36) | 1.23 (1.09, 1.40)
HIV Fixed-Dose Combination Regimen
Elvitegravir/ cobicistat/ emtricitabine/ tenofovir disoproxil fumarate | Elvitegravir 150 mg once daily | EBR/GZR | 50 mg / 100 mg once daily | 22 | 1.10 (1.00, 1.21) | 1.02 (0.93, 1.11) | 1.31 (1.11, 1.55)
Elvitegravir/ cobicistat/ emtricitabine/ tenofovir disoproxil fumarate | Cobicistat 150 mg once daily | EBR/GZR | 50 mg / 100 mg once daily | 22 | 1.49 (1.42, 1.57) | 1.39 (1.29, 1.50) | --
Elvitegravir/ cobicistat/ emtricitabine/ tenofovir disoproxil fumarate | Emtricitabine 200 mg once daily | EBR/GZR | 50 mg / 100 mg once daily | 22 | 1.07 (1.03, 1.10) | 0.96 (0.90, 1.02) | 1.19 (1.13, 1.25)
Elvitegravir/ cobicistat/ emtricitabine/ tenofovir disoproxil fumarate | Tenofovir disoproxil fumarate 300 mg once daily | EBR/GZR | 50 mg / 100 mg once daily | 22 | 1.18 (1.13, 1.24) | 1.25 (1.14, 1.37) | 1.20 (1.15, 1.26)
Immunosuppressant
Cyclosporine | Cyclosporine 400 mg single-dose | EBR + GZR | 50 mg + 200 mg once daily | 14 | 0.96 (0.90, 1.02) | 0.90 (0.85, 0.97) | 1.00 (0.92, 1.08)
Mycophenolic acid | Mycophenolate mofetil 1000 mg single-dose | EBR + GZR | 50 mg + 200 mg once daily | 14 | 0.95 (0.87, 1.03) | 0.85 (0.67, 1.07) | --
Prednisolone | Prednisone 40 mg single-dose | EBR + GZR | 50 mg + 200 mg once daily | 14 | 1.08 (1.01, 1.16) | 1.04 (0.99, 1.09) | --
Prednisone | Prednisone 40 mg single-dose | EBR + GZR | 50 mg + 200 mg once daily | 14 | 1.08 (1.00, 1.17) | 1.05 (1.00, 1.10) | --
Tacrolimus | Tacrolimus 2 mg single-dose | EBR + GZR | 50 mg + 200 mg once daily | 16 | 1.43 (1.24, 1.64) | 0.60 (0.52, 0.69) | 1.70 (1.49, 1.94)
Oral Contraceptive
Ethinyl estradiol (EE) | 0.03 mg EE/ 0.15 mg LNG single-dose | EBR | 50 mg once daily | 20 | 1.01 (0.97, 1.05) | 1.10 (1.05, 1.16) | --
Ethinyl estradiol (EE) | 0.03 mg EE/ 0.15 mg LNG single-dose | GZR | 200 mg once daily | 20 | 1.10 (1.05, 1.14) | 1.05 (0.98, 1.12) | --
Levonorgestrel (LNG) | 0.03 mg EE/ 0.15 mg LNG single-dose | EBR | 50 mg once daily | 20 | 1.14 (1.04, 1.24) | 1.02 (0.95, 1.08) | --
Levonorgestrel (LNG) | 0.03 mg EE/ 0.15 mg LNG single-dose | GZR | 200 mg once daily | 20 | 1.23 (1.15, 1.32) | 0.93 (0.84, 1.03) | --
Opioid Substitution Therapy
Buprenorphine | Buprenorphine 8 mg/Naloxone 2 mg single-dose | EBR | 50 mg once daily | 15 | 0.98 (0.89, 1.08) | 0.94 (0.82, 1.08) | 0.98 (0.88, 1.09)
Buprenorphine | Buprenorphine 8-24 mg/ Naloxone 2-6 mg once daily | GZR | 200 mg once daily | 12 | 0.98 (0.81, 1.19) | 0.90 (0.76, 1.07) | --
R-Methadone | Methadone 20-120 mg once daily | EBR | 50 mg once daily | 10 | 1.03 (0.92, 1.15) | 1.07 (0.95, 1.20) | 1.10 (0.96, 1.26)
R-Methadone | Methadone 20-150 mg once daily | GZR | 200 mg once daily | 12 | 1.09 (1.02, 1.17) | 1.03 (0.96, 1.11) | --
S-Methadone | Methadone 20-120 mg once daily | EBR | 50 mg once daily | 10 | 1.09 (0.94, 1.26) | 1.09 (0.95, 1.25) | 1.20 (0.98, 1.47)
S-Methadone | Methadone 20-150 mg once daily | GZR | 200 mg once daily | 12 | 1.23 (1.12, 1.35) | 1.15 (1.07, 1.25) | --
Statin
Atorvastatin | Atorvastatin 10 mg single-dose | EBR + GZR | 50 mg + 200 mg once daily | 16 | 1.94 (1.63, 2.33) | 4.34 (3.10, 6.07) | 0.21 (0.17, 0.26)
Pitavastatin | Pitavastatin 1 mg single-dose | GZR | 200 mg once daily | 9 | 1.11 (0.91, 1.34) | 1.27 (1.07, 1.52) | --
Pravastatin | Pravastatin 40 mg single-dose | EBR + GZR | 50 mg + 200 mg once daily | 12 | 1.33 (1.09, 1.64) [N=10] | 1.28 (1.05, 1.55) | --
Rosuvastatin | Rosuvastatin 10 mg single-dose | EBR + GZR | 50 mg + 200 mg once daily | 12 | 2.26 (1.89, 2.69) [N=8] | 5.49 (4.29, 7.04) | 0.98 (0.84, 1.13)
Abbreviations: EBR, elbasvir; GZR, grazoprevir; EBR + GZR, administration of EBR and GZR as separate tablets; EBR/GZR, administration of EBR and GZR as a single fixed-dose combination tablet

12.4 Microbiology

Mechanism of Action

ZEPATIER combines two direct-acting antiviral agents with distinct mechanisms of action and non-overlapping resistance profiles to target HCV at multiple steps in the viral lifecycle.

Elbasvir is an inhibitor of HCV NS5A, which is essential for viral RNA replication and virion assembly. The mechanism of action of elbasvir has been characterized based on cell culture antiviral activity and drug resistance mapping studies.

Grazoprevir is an inhibitor of the HCV NS3/4A protease which is necessary for the proteolytic cleavage of the HCV encoded polyprotein (into mature forms of the NS3, NS4A, NS4B, NS5A, and NS5B proteins) and is essential for viral replication. In a biochemical assay, grazoprevir inhibited the proteolytic activity of the recombinant HCV genotype 1a, 1b, and 4a NS3/4A protease enzymes with IC50 values of 7 pM, 4 pM, and 62 pM, respectively.

Antiviral Activity

In HCV replicon assays, the EC50 values of elbasvir against full-length replicons from genotypes 1a, 1b, and 4, were 4 pM, 3 pM, and 0.3 pM, respectively. The median EC50 values of elbasvir against chimeric replicons encoding NS5A sequences from clinical isolates were 5 pM for genotype 1a (range 3-9 pM; N=5), 9 pM for genotype 1b (range 5-10 pM; N=4), 0.2 pM for genotype 4a (range 0.2-0.2 pM; N=2), 3,600 pM for genotype 4b (range 17 pM-34,000 pM; N=3), 0.45 pM for genotype 4d (range 0.4-0.5 pM; N=2), 1.9 pM for genotype 4f (N=1), 36.3 pM for genotype 4g (range 0.6-72 pM; N=2), 0.6 pM for genotype 4m (range 0.4-0.7 pM; N=2), 2.2 pM for genotype 4o (N=1), and 0.5 pM for genotype 4q (N=1).

In HCV replicon assays, the EC50 values of grazoprevir against full-length replicons from genotypes 1a, 1b, and 4, were 0.4 nM, 0.5 nM, and 0.3 nM, respectively. The median EC50 values of grazoprevir against chimeric replicons encoding NS3/4A sequences from clinical isolates were 0.8 nM for genotype 1a (range 0.4-5.1 nM; N=10), 0.3 nM for genotype 1b (range 0.2-5.9 nM; N=9), 0.3 nM for genotype 4a (N=1), 0.16 nM for genotype 4b (range 0.11-0.2 nM; N=2), and 0.24 nM for genotype 4g (range 0.15-0.33 nM; N=2).

Combination Antiviral Activity

Evaluation of elbasvir in combination with grazoprevir or ribavirin showed no antagonistic effect in reducing HCV RNA levels in replicon cells. Evaluation of grazoprevir in combination with ribavirin showed no antagonistic effect in reducing HCV RNA levels in replicon cells.

Resistance

In Cell Culture

HCV replicons with reduced susceptibility to elbasvir and grazoprevir have been selected in cell culture for genotypes 1a, 1b, and 4 which resulted in the emergence of resistance-associated amino acid substitutions in NS5A or NS3, respectively. The majority of amino acid substitutions in NS5A or NS3 selected in cell culture or identified in Phase 2b and 3 clinical trials were phenotypically characterized in genotype 1a, 1b, or 4 replicons.

For elbasvir, in HCV genotype 1a replicons, single NS5A substitutions M28A/G/T, Q30D/E/H/K/R, L31M/V, H58D, and Y93C/H/N reduced elbasvir antiviral activity by 1.5- to 2,000-fold. In genotype 1b replicons, single NS5A substitutions L28M, L31F, and Y93H reduced elbasvir antiviral activity by 2- to 17-fold. In genotype 4 replicons, single NS5A substitutions L30S, M31V, and Y93H reduced elbasvir antiviral activity by 3- to 23-fold. In general, in HCV genotype 1a, 1b, or 4 replicons, combinations of elbasvir resistance-associated substitutions further reduced elbasvir antiviral activity.

For grazoprevir, in HCV genotype 1a replicons, single NS3 substitutions Y56H, R155K, A156G/T/V, and D168A/E/G/N/S/V/Y reduced grazoprevir antiviral activity by 2- to 81-fold; V36L/M, Q80K/R, or V107I single substitutions had no impact on grazoprevir antiviral activity in cell culture. In genotype 1b replicons, single NS3 substitutions F43S, Y56F, V107I, A156S/T/V, and D168A/G/V reduced grazoprevir antiviral activity by 1.5- to 375-fold. In genotype 4 replicons, single NS3 substitutions D168A/V reduced grazoprevir antiviral activity by 110- to 320-fold. In general, in HCV genotype 1a, 1b, or 4 replicons, combinations of grazoprevir resistance-associated substitutions further reduced grazoprevir antiviral activity.

In Clinical Studies

In a pooled analysis of subjects treated with regimens containing ZEPATIER or elbasvir + grazoprevir with or without ribavirin in Phase 2 and 3 clinical trials, resistance analyses of both drug targets were conducted for 50 subjects who experienced virologic failure and had sequence data available (6 with on-treatment virologic failure, 44 with post-treatment relapse). Treatment-emergent substitutions observed in the viral populations of these subjects based on HCV genotypes and subtypes are shown in Table 11. Treatment-emergent NS5A substitutions were detected in 30/37 (81%) genotype 1a-, 7/8 (88%) genotype 1b-, and 5/5 (100%) genotype 4-infected subjects. The most common treatment-emergent NS5A substitutions in genotype 1a were at position Q30 (n=22). Treatment-emergent NS3 substitutions were detected in 29/37 (78%) genotype 1a-, 2/8 (25%) genotype 1b-, and 2/5 (40%) genotype 4-infected subjects. The most common treatment-emergent NS3 substitutions in genotype 1a were at position D168 (n=18). Treatment-emergent substitutions were detected in both HCV drug targets in 23/37 (62%) genotype 1a-, 1/8 (13%) genotype 1b-, and 2/5 (40%) genotype 4-infected subjects.

Table 11: Treatment-Emergent Amino Acid Substitutions Among Virologic Failures in the Pooled Analysis of ZEPATIER with and without Ribavirin Regimens in Phase 2 and Phase 3 Clinical Trials
Target | Genotype 1a N = 37 | Genotype 1b N = 8 | Genotype 4 N = 5
NS5A | M28A/G/T, Q30H/K/R/Y, L31F/M/V, H58D, Y93H/N/S | L28M, L31F/V, Y93H | L28S/T, M31I/V, P58D, Y93H
NS3 | V36L/M, Y56H, V107I, R155I/K, A156G/T/V, V158A, D168A/G/N/V/Y | Y56F, V107I, A156T | A156M/T/V, D168A/G, V170I

Persistence of Resistance-Associated Substitutions

The persistence of elbasvir and grazoprevir treatment-emergent amino acid substitutions in NS5A, and NS3, respectively, was assessed in HCV genotype 1-infected subjects in Phase 2 and 3 trials whose virus had treatment-emergent resistance-associated substitutions in the drug target, and with available data through at least 24 weeks post-treatment using population nucleotide sequence analysis.

Viral populations with treatment-emergent NS5A resistance-associated substitutions were generally more persistent than those with NS3 resistance-associated substitutions. Among genotype 1a-infected subjects, NS5A resistance-associated substitutions persisted at detectable levels at follow-up week 12 in 95% (35/37) of subjects and in 100% (9/9) of subjects with follow-up week 24 data. Among genotype 1b-infected subjects, NS5A resistance-associated substitutions persisted at detectable levels in 100% (7/7) of subjects at follow-up week 12 and in 100% (3/3) of subjects with follow-up week 24 data.

Among genotype 1a-infected subjects, NS3 resistance-associated substitutions persisted at detectable levels at follow-up week 24 in 31% (4/13) of subjects. Among genotype 1b-infected subjects, NS3 resistance-associated substitutions persisted at detectable levels at follow-up week 24 in 50% (1/2) of subjects.

Due to the limited number of genotype 4-infected subjects with treatment-emergent NS5A and NS3 resistance-associated substitutions, trends in persistence of treatment-emergent substitutions in this genotype could not be established.

The lack of detection of a virus containing a resistance-associated substitution does not necessarily indicate that viral populations carrying that substitution have declined to a background level that may have existed prior to treatment. The long-term clinical impact of the emergence or persistence of virus containing ZEPATIER-resistance-associated substitutions is unknown.

Effect of Baseline HCV Amino Acid Polymorphisms on Treatment Response in Genotype 1-Infected Subjects

Analyses using population nucleotide sequencing were conducted to explore the association between NS5A or NS3 amino acid polymorphisms and treatment response among treatment-naïve and treatment-experienced genotype 1-infected subjects. Baseline NS5A polymorphisms at resistance-associated positions (focusing on any change from subtype reference at NS5A amino acid positions 28, 30, 31, or 93) were evaluated. Baseline NS3 polymorphisms at positions 36, 54, 55, 56, 80, 107, 122, 132, 155, 156, 158, 168, 170, or 175 were evaluated. Analyses of SVR12 rates pooled data from subjects naïve to direct-acting antivirals and who received ZEPATIER with or without ribavirin in Phase 3 clinical trials, and censored subjects who did not achieve SVR12 for reasons unrelated to virologic failure.

Genotype 1a

In Clinical Studies

In genotype 1a-infected subjects, the presence of one or more HCV NS5A amino acid polymorphisms at position M28, Q30, L31, or Y93 was associated with reduced efficacy of ZEPATIER for 12 weeks (Table 12), regardless of prior treatment history or cirrhosis status. The prevalence of polymorphisms at any of these positions in genotype 1a-infected subjects was 11% (62/561) overall, and 12% (37/309) specifically for subjects in the U.S. across Phase 2 and Phase 3 clinical trials evaluating ZEPATIER for 12 weeks or ZEPATIER plus ribavirin for 16 weeks. The prevalence of polymorphisms at these positions in genotype 1a-infected subjects was 6% (35/561) at position M28, 2% (11/561) at position Q30, 3% (15/561) at position L31, and 2% (10/561) at position Y93. Polymorphisms at NS5A position H58 were common (10%) and were not associated with reduced ZEPATIER efficacy, except for a single virologic failure subject whose virus had baseline M28V and H58D polymorphisms.

The SVR12 rates for subjects treated with ZEPATIER for 12 weeks were 88% (29/33) for subjects with M28V/T/L polymorphisms (n=29, 3, and 1, respectively), 40% (4/10) for subjects with Q30H/R/L polymorphisms (n=5, 3, and 2, respectively), 38% (5/13) for subjects with an L31M polymorphism, and 63% (5/8) for subjects with Y93C/H/N/S polymorphisms (n=3, 3, 1, and 1, respectively). Although clinical trial data are limited, among genotype 1a-infected subjects with these NS5A polymorphisms who received ZEPATIER plus ribavirin for 16 weeks, six out of six subjects achieved SVR12. The specific NS5A polymorphisms observed in subjects treated with ZEPATIER plus ribavirin for 16 weeks included M28V (n=2), Q30H (n=1), L31M (n=2), or Y93C/H (n=1 each).

Table 12: Clinical Trial Data: SVR12 in HCV Genotype 1a-Infected Subjects without or with Baseline NS5A Polymorphisms
NS5A Polymorphism Status | ZEPATIER 12 Weeks SVR12 % (n/N) | ZEPATIER + RBV 16 Weeks SVR12 % (n/N)
Without baseline NS5A polymorphism (M28, Q30, L31, or Y93) | 98% (441/450) | 100% (49/49)
With baseline NS5A polymorphism (M28 [Any change from GT1a reference.] , Q30, L31, or Y93) | 70% (39/56) | 100% (6/6)

There are insufficient clinical trial data to determine the impact of HCV NS5A amino acid polymorphisms in treatment-experienced subjects who failed prior PegIFN + RBV + HCV protease inhibitor therapy and received ZEPATIER with ribavirin.

In genotype 1a-infected subjects, the NS3 Q80K polymorphism did not impact treatment response. Polymorphisms at other NS3 resistance-associated positions were uncommon and were not associated with reduced treatment efficacy.

In Postmarketing Observational Studies

Effectiveness (SVR12 rates) in observational studies can be subject to certain biases and confounding factors that cannot be accounted for in the analyses, in part due to the nature of the study designs and populations under study.

Protocol 095

In Protocol 095, a sub-study of a prospective, observational comparative study, effectiveness of treatment with ZEPATIER plus ribavirin for 16 weeks was assessed in 29 HCV genotype 1a-infected patients with 1 or more baseline NS5A polymorphisms at amino acid positions M28, Q30, L31, and/or Y93. Overall, the SVR12 rate for patients with 1 or more baseline NS5A polymorphisms at any of the 4 amino acid positions was 93% (27/29). 23 patients had a NS5A polymorphism at a single amino acid position at baseline. The SVR12 rates for patients with a single polymorphism at amino acid position M28, Q30, L31, or Y93 were 100% (14/14), 100% (1/1), 33% (1/3), and 100% (5/5), respectively. Six patients had NS5A polymorphisms at more than 1 amino acid position (M28, Q30, L31, and/or Y93) at baseline. The SVR12 rate for these patients was 100% (6/6).

VA NS5A Cohort Study

In a retrospective Veterans Administration (VA) NS5A cohort study, effectiveness of treatment with ZEPATIER plus ribavirin for 16 weeks was assessed in 93 HCV genotype 1a-infected patients with 1 or more baseline NS5A polymorphisms at amino acid positions M28, Q30, L31, and/or Y93. Overall, the SVR12 rate for patients with 1 or more baseline NS5A polymorphisms at any of the 4 amino acid positions was 81% (75/93). 65 patients had a NS5A polymorphism at a single amino acid position at baseline. The SVR12 rates for patients with a single polymorphism at amino acid position M28, Q30, L31, or Y93 were 94% (16/17), 100% (8/8), 84% (16/19), and 81% (17/21), respectively. 28 patients had NS5A polymorphisms at more than 1 amino acid position (M28, Q30, L31, and/or Y93) at baseline. The SVR12 rate for these patients was 64% (18/28).

Genotype 1b

In Clinical Studies

In genotype 1b-infected subjects treated with ZEPATIER for 12 weeks, SVR12 rates (non-virologic failure-censored) were 94% (48/51) and 99% (247/248) for those with and without one or more NS5A polymorphisms at position 28, 30, 31, or 93.

In genotype 1b-infected subjects, baseline NS3 polymorphisms did not impact treatment response.

Effect of Baseline HCV Polymorphisms on Treatment Response in Genotype 4-Infected Subjects

Phylogenetic analysis of HCV sequences from genotype 4-infected subjects (n=71) in the pooled analyses of subjects (non-virologic failure-censored) treated with regimens containing ZEPATIER or elbasvir + grazoprevir with or without ribavirin in Phase 2 and 3 clinical trials identified 4 HCV genotype 4 subtypes (4a, 4d, 4k, 4o). Most subjects were infected with either subtype 4a (42%) or 4d (51%); 1 to 2 subjects were infected with each of the other genotype 4 subtypes. Among subjects enrolled at U.S. study sites, 11/13 (85%) were infected with HCV subtype 4a. There were two subjects infected with HCV subtype 4d who experienced virologic failure with the regimen containing grazoprevir and elbasvir.

In genotype 4-infected subjects, SVR12 rates for subjects with baseline NS5A polymorphisms (any change from reference at NS5A amino acid positions 28, 30, 31, 58, and 93 by population nucleotide sequencing) were 100% (28/28) and for subjects without baseline NS5A polymorphisms were 95% (41/43).

In genotype 4-infected subjects, SVR12 rates for subjects with baseline NS3 polymorphisms (any change from reference at NS3 amino acid positions 36, 54, 55, 56, 80, 107, 122, 132, 155, 156, 158, 168, 170, and 175 by population nucleotide sequencing) were 100% (18/18) and for subjects without baseline NS3 polymorphisms were 96% (51/53).

Cross Resistance

Cross resistance is possible among NS5A inhibitors and NS3/4A protease inhibitors by class. Elbasvir and grazoprevir are fully active against viral populations with substitutions conferring resistance to NS5B inhibitors.

In the C-SALVAGE trial, subjects with genotype 1 infection who had failed prior treatment with boceprevir (n=28), simeprevir (n=8), or telaprevir (n=43) in combination with PegIFN + RBV received EBR 50 mg once daily + GZR 100 mg once daily + RBV for 12 weeks. There are limited data to determine the impact of HCV NS3 resistance-associated substitutions detected at baseline in treatment-experienced subjects who failed prior PegIFN + RBV + HCV protease inhibitor therapy and received ZEPATIER with ribavirin. SVR was achieved in 88% (21/24) of genotype 1a and genotype 1b infected subjects with NS3 resistance-associated substitutions detected at baseline. Specific NS3 substitutions observed at baseline included one or more of the following: V36L/M (n=8), T54S (n=4), S122G/T (n=9), R155K/T (n=9), A156S/T (n=1), and D168E/N (n=3). SVR was 100% (55/55) in subjects without baseline NS3 resistance substitutions. The 3 virologic failure subjects had the following NS3 or NS5A substitutions/polymorphisms at baseline: NS3 R155T/D168N, NS3 R155K plus NS5A H58D, and NS3 T54S plus NS5A L31M.

The efficacy of ZEPATIER has not been established in patients who have previously failed treatment with other regimens that included an NS5A inhibitor.

13 NONCLINICAL TOXICOLOGY

13.1 Carcinogenesis, Mutagenesis, Impairment of Fertility

Carcinogenesis and Mutagenesis

Elbasvir and grazoprevir were not genotoxic in a battery of in vitro or in vivo assays, including microbial mutagenesis, chromosomal aberration in Chinese Hamster Ovary cells, and in in vivo rat micronucleus assays.

Carcinogenicity studies with elbasvir or grazoprevir have not been conducted.

If ZEPATIER is administered in a regimen containing ribavirin, the information for ribavirin on carcinogenesis and mutagenesis also applies to this combination regimen. Refer to the ribavirin prescribing information for information on carcinogenesis and mutagenesis.

Impairment of Fertility

No effects on mating, female or male fertility, or early embryonic development were observed in rats at up to the highest dose tested. Systemic exposures (AUC) to elbasvir and grazoprevir were approximately 8 and 114 times, respectively, the exposure in humans at the recommended human dose.

If ZEPATIER is administered with ribavirin, the information for ribavirin on impairment of fertility also applies to this combination regimen. Refer to the ribavirin prescribing information for information on impairment of fertility.

14 CLINICAL STUDIES

14.1 Overview of Clinical Trials

The efficacy of ZEPATIER was assessed in 2 placebo-controlled trials and 4 uncontrolled Phase 2 and 3 clinical trials in 1401 subjects with genotype (GT) 1, 4, or 6 and in 1 clinical trial in 22 pediatric subjects with GT 1 or 4 chronic hepatitis C virus infection with compensated liver disease (with or without cirrhosis). An overview of the 6 trials (n=1373) contributing to the assessment of efficacy in genotype 1 or 4 is provided in Table 13. C-EDGE TN, C-EDGE COINFECTION, C-SCAPE, and C-EDGE TE also included subjects with genotype 6 HCV infection (n=28). Because ZEPATIER is not indicated for genotype 6 infection, results in patients with genotype 6 infection are not included in Clinical Studies (14).

Table 13: Trials Conducted with ZEPATIER
Trial | Population | Study Groups and Duration (Number of Subjects Treated)
C-EDGE TN (double-blind) | GT 1, 4 TN with or without cirrhosis | - ZEPATIER for 12 weeks (N=306) - Placebo for 12 weeks (N=102)
C-EDGE COINFECTION (open-label) | GT 1, 4 TN with or without cirrhosis HCV/HIV-1 co-infection | - ZEPATIER for 12 weeks (N=217)
C-SURFER (double-blind) | GT 1 TN or TE with or without cirrhosis Severe Renal Impairment including Hemodialysis | - EBR [EBR = elbasvir 50 mg; GZR = grazoprevir 100 mg; EBR + GZR = co-administered as single agents.] + GZR for 12 weeks (N=122) - Placebo for 12 weeks (N=113)
C-SCAPE (open-label) | GT 4 TN without cirrhosis | - EBR + GZR for 12 weeks (N=10) - EBR + GZR + RBV for 12 weeks (N=10)
C-EDGE TE (open-label) | GT 1, 4 TE with or without cirrhosis with or without HCV/HIV-1 co-infection | - ZEPATIER for 12 or 16 weeks (N=105 and 101, respectively) - ZEPATIER + RBV for 12 or 16 weeks (N=104 and 104, respectively)
C-SALVAGE (open-label) | GT 1 TE with HCV protease inhibitor regimen [Failed prior treatment with boceprevir, telaprevir, or simeprevir in combination with PegIFN + RBV.] with or without cirrhosis | - EBR + GZR + RBV for 12 weeks (N=79)
MK-5172-079 (open-label) | GT 1, 4 TN or TE pediatric subjects | - ZEPATIER for 12 weeks (N=22; 12 years to less than 18 years)
GT = Genotype
TN = Treatment-Naïve
TE = Treatment-Experienced (failed prior treatment with interferon [IFN] or peginterferon alfa [PegIFN] with or without ribavirin [RBV] or were intolerant to prior therapy).

ZEPATIER was administered once daily by mouth in these trials. For subjects who received ribavirin (RBV), the RBV dosage was weight-based (less than 66 kg = 800 mg per day, 66 to 80 kg = 1000 mg per day, 81 to 105 kg = 1200 mg per day, greater than 105 kg = 1400 mg per day) administered by mouth in two divided doses with food.

Sustained virologic response (SVR) was the primary endpoint in all trials and was defined as HCV RNA less than lower limit of quantification (LLOQ) at 12 weeks after the cessation of treatment (SVR12). Serum HCV RNA values were measured during these clinical trials using the COBAS AmpliPrep/COBAS Taqman HCV test (version 2.0) with an LLOQ of 15 HCV RNA IU per mL, with the exception of C-SCAPE where the assay had an LLOQ of 25 HCV RNA IU per mL.

14.2 Clinical Trials in Treatment-Naïve Subjects with Genotype 1 HCV (C-EDGE TN and C-EDGE COINFECTION)

The efficacy of ZEPATIER in treatment-naïve subjects with genotype 1 chronic hepatitis C virus infection with or without cirrhosis was demonstrated in the C-EDGE TN and C-EDGE COINFECTION trials.

C-EDGE TN was a randomized, double-blind, placebo-controlled trial in treatment-naïve subjects with genotype 1 or 4 infection with or without cirrhosis. Subjects were randomized in a 3:1 ratio to: ZEPATIER for 12 weeks (immediate treatment group) or placebo for 12 weeks followed by open-label treatment with ZEPATIER for 12 weeks (deferred treatment group). Among subjects with genotype 1 infection randomized to the immediate treatment group, the median age was 55 years (range: 20 to 78); 56% of the subjects were male; 61% were White; 20% were Black or African American; 8% were Hispanic or Latino; mean body mass index was 26 kg/m^2; 72% had baseline HCV RNA levels greater than 800,000 IU per mL; 24% had cirrhosis; 67% had non-C/C IL28B alleles (CT or TT); and 55% had genotype 1a and 45% had genotype 1b chronic HCV infection.

C-EDGE COINFECTION was an open-label, single-arm trial in treatment-naïve HCV/HIV-1 co-infected subjects with genotype 1 or 4 infection with or without cirrhosis. Subjects received ZEPATIER for 12 weeks. Among subjects with genotype 1 infection, the median age was 50 years (range: 21 to 71); 85% of the subjects were male; 75% were White; 19% were Black or African American; 6% were Hispanic or Latino; mean body mass index was 25 kg/m^2; 59% had baseline HCV RNA levels greater than 800,000 IU per mL; 16% had cirrhosis; 65% had non-C/C IL28B alleles (CT or TT); and 76% had genotype 1a, 23% had genotype 1b, and 1% had genotype 1-Other chronic HCV infection.

Table 14 presents treatment outcomes for ZEPATIER in treatment-naïve subjects with genotype 1 infection from C-EDGE TN (immediate treatment group) and C-EDGE COINFECTION. For treatment outcomes for ZEPATIER in genotype 4 infection, [see Clinical Studies (14.5)].

Table 14: C-EDGE TN and C-EDGE COINFECTION: SVR12 in Treatment-Naïve Subjects with or without Cirrhosis with Genotype 1 HCV Treated with ZEPATIER for 12 Weeks
Trial | C-EDGE TN (Immediate Treatment Group) | C-EDGE COINFECTION (HCV/HIV-1 Co-Infection)
Regimen | ZEPATIER 12 Weeks N=288 | ZEPATIER 12 Weeks N=189
SVR in Genotype 1 | 95% (273/288) | 95% (179/189)
Outcome for subjects without SVR
On-treatment Virologic Failure [Includes subjects with virologic breakthrough.] | <1% (1/288) | 0% (0/189)
Relapse | 3% (10/288) | 3% (6/189)
Other [Other includes subjects who discontinued due to adverse event, lost to follow-up, or subject withdrawal.] | 1% (4/288) | 2% (4/189)
SVR by Genotype 1 Subtypes
GT 1a [For the impact of baseline NS5A polymorphisms on SVR12, [see Microbiology (12.4), Table 12].] | 92% (144/157) | 94% (136/144)
GT 1b [Includes genotype 1 subtypes other than 1a or 1b.] | 98% (129/131) | 96% (43/45)
SVR by Cirrhosis status
Non-cirrhotic | 94% (207/220) | 94% (148/158)
Cirrhotic | 97% (66/68) | 100% (31/31)

14.3 Clinical Trials in Treatment-Experienced Subjects with Genotype 1 HCV

Treatment-Experienced Subjects who Failed Prior PegIFN with RBV Therapy (C-EDGE TE)

C-EDGE TE was a randomized, open-label comparative trial in subjects with genotype 1 or 4 infection, with or without cirrhosis, with or without HCV/HIV-1 co-infection, who had failed prior therapy with PegIFN + RBV therapy. Subjects were randomized in a 1:1:1:1 ratio to one of the following treatment groups: ZEPATIER for 12 weeks, ZEPATIER + RBV for 12 weeks, ZEPATIER for 16 weeks, or ZEPATIER + RBV for 16 weeks. Among subjects with genotype 1 infection, the median age was 57 years (range: 19 to 77); 64% of the subjects were male; 67% were White; 18% were Black or African American; 9% were Hispanic or Latino; mean body mass index was 28 kg/m^2; 78% had baseline HCV RNA levels greater than 800,000 IU/mL; 34% had cirrhosis; 79% had non-C/C IL28B alleles (CT or TT); and 60% had genotype 1a, 39% had genotype 1b, and 1% had genotype 1-Other chronic HCV infection.

Treatment outcomes in genotype 1 subjects treated with ZEPATIER for 12 weeks or ZEPATIER with RBV for 16 weeks are presented in Table 15. Treatment outcomes with ZEPATIER with RBV for 12 weeks or without RBV for 16 weeks are not shown because these regimens are not recommended in PegIFN/RBV-experienced genotype 1 patients. For treatment outcomes for ZEPATIER in genotype 4 infection, [see Clinical Studies (14.5)].

Table 15: C-EDGE TE: SVR12 in Treatment-Experienced Subjects who Failed Prior PegIFN with RBV with or without Cirrhosis, with or without HCV/HIV-1 Co-infection with Genotype 1 HCV Treated with ZEPATIER for 12 Weeks or ZEPATIER with Ribavirin for 16 Weeks
Regimen | ZEPATIER 12 weeks N=96 | ZEPATIER + RBV 16 weeks N=96
SVR in Genotype 1 | 94% (90/96) | 97% (93/96)
Outcome for subjects without SVR
On-treatment Virologic Failure [Includes subjects with virologic breakthrough or rebound.] | 0% (0/96) | 0% (0/96)
Relapse | 5% (5/96) | 0% (0/96)
Other [Other includes subjects who discontinued due to adverse event, lost to follow-up, or subject withdrawal.] | 1% (1/96) | 3% (3/96)
SVR by Genotype 1 Subtypes
GT 1a [For the impact of baseline NS5A polymorphisms on SVR, [see Microbiology (12.4), Table 12].] | 90% (55/61) | 95% (55/58)
GT 1b [Includes genotype 1 subtypes other than 1a or 1b.] | 100% (35/35) | 100% (38/38)
SVR by Cirrhosis status
Non-cirrhotic | 94% (61/65) | 95% (61/64)
Cirrhotic | 94% (29/31) | 100% (32/32)
SVR by Response to Prior HCV Therapy
On-treatment Virologic Failure [Includes prior null responders and partial responders.] | 90% (57/63) | 95% (58/61)
Relapser | 100% (33/33) | 100% (35/35)

Treatment-Experienced Subjects who Failed Prior PegIFN + RBV + HCV Protease Inhibitor Therapy (C-SALVAGE)

C-SALVAGE was an open-label single-arm trial in subjects with genotype 1 infection, with or without cirrhosis, who had failed prior treatment with boceprevir, simeprevir, or telaprevir in combination with PegIFN + RBV. Subjects received EBR 50 mg once daily + GZR 100 mg once daily + RBV for 12 weeks. Subjects had a median age of 55 years (range: 23 to 75); 58% of the subjects were male; 97% were White; 3% were Black or African American; 15% were Hispanic or Latino; mean body mass index was 28 kg/m^2; 63% had baseline HCV RNA levels greater than 800,000 IU/mL; 43% had cirrhosis; and 97% had non-C/C IL28B alleles (CT or TT); 46% had baseline NS3 resistance-associated substitutions.

Overall SVR was achieved in 96% (76/79) of subjects receiving EBR + GZR + RBV for 12 weeks. Four percent (3/79) of subjects did not achieve SVR due to relapse. Treatment outcomes were consistent in genotype 1a and genotype 1b subjects, in subjects with different response to previous HCV therapy, and in subjects with or without cirrhosis. Treatment outcomes were generally consistent in subjects with or without NS3 resistance-associated substitutions at baseline, although limited data are available for subjects with specific NS3 resistance-associated substitutions [see Microbiology (12.4)].

14.4 Clinical Trial in Subjects with Genotype 1 HCV and Severe Renal Impairment including Subjects on Hemodialysis (C-SURFER)

C-SURFER was a randomized, double-blind, placebo-controlled trial in subjects with genotype 1 infection, with or without cirrhosis, with chronic kidney disease (CKD) Stage 4 (eGFR 15-29 mL/min/1.73 m^2) or CKD Stage 5 (eGFR <15 mL/min/1.73 m^2), including subjects on hemodialysis, who were treatment-naïve or who had failed prior therapy with IFN or PegIFN ± RBV therapy. Subjects were randomized in a 1:1 ratio to one of the following treatment groups: EBR 50 mg once daily + GZR 100 mg once daily for 12 weeks (immediate treatment group) or placebo for 12 weeks followed by open-label treatment with EBR + GZR for 12 weeks (deferred treatment group). In addition, 11 subjects received open-label EBR + GZR for 12 weeks (intensive pharmacokinetic [PK] group). Subjects randomized to the immediate treatment group and intensive PK group had a median age of 58 years (range: 31 to 76); 75% of the subjects were male; 50% were White; 45% were Black or African American; 11% were Hispanic or Latino; 57% had baseline HCV RNA levels greater than 800,000 IU/mL; 6% had cirrhosis; and 72% had non-C/C IL28B alleles (CT or TT).

Treatment outcomes in subjects treated with ZEPATIER for 12 weeks in the pooled immediate treatment group and intensive PK group are presented in Table 16.

Table 16: C-SURFER: SVR12 in Subjects with Severe Renal Impairment including Subjects on Hemodialysis who were Treatment-Naïve or had Failed Prior IFN or PegIFN ± RBV, with or without Cirrhosis, with Genotype 1 HCV Treated with ZEPATIER for 12 Weeks
Regimen | EBR + GZR 12 weeks (Immediate Treatment Group) N=122 [Includes subjects (n=11) in the intensive PK group.]
Overall SVR | 94% (115/122) [SVR was achieved in 99% (115/116) of subjects in the pre-specified primary analysis population, which excluded subjects not receiving at least one dose of study treatment and those with missing data due to death or early study discontinuation for reasons unrelated to treatment response.]
Outcome for subjects without SVR
On-treatment Virologic Failure | 0% (0/122)
Relapse | <1% (1/122)
Other [Other includes subjects who discontinued due to adverse event, lost to follow-up, or subject withdrawal.] | 5% (6/122)
SVR by Genotype
GT 1a | 97% (61/63)
GT 1b [Includes genotype 1 subtypes other than 1a or 1b.] | 92% (54/59)
SVR by Cirrhosis status
No | 95% (109/115)
Yes | 86% (6/7)
SVR by Prior HCV Treatment Status
Treatment-naïve | 95% (96/101)
Treatment-experienced | 90% (19/21)
SVR by Dialysis Status
No | 97% (29/30)
Yes | 93% (86/92)
SVR by Chronic Kidney Disease Stage
Stage 4 | 100% (22/22)
Stage 5 | 93% (93/100)

14.5 Clinical Trials with Genotype 4 HCV

The efficacy of ZEPATIER in subjects with genotype 4 chronic HCV infection was demonstrated in C-EDGE TN, C-EDGE COINFECTION, C-EDGE TE, and C-SCAPE. C-SCAPE was a randomized, open-label trial which included treatment-naïve subjects with genotype 4 infection without cirrhosis. Subjects were randomized in a 1:1 ratio to EBR 50 mg once daily + GZR 100 mg once daily for 12 weeks or EBR 50 mg once daily + GZR 100 mg once daily + RBV for 12 weeks. In these combined studies in subjects with genotype 4 infection, 64% were treatment-naïve; 66% of the subjects were male; 87% were White; 10% were Black or African American; 22% had cirrhosis; and 30% had HCV/HIV-1 co-infection.

In C-SCAPE, C-EDGE TN, and C-EDGE COINFECTION trials combined, a total of 66 genotype 4 treatment-naïve subjects received ZEPATIER or EBR + GZR for 12 weeks. In these combined trials, SVR12 among subjects treated with ZEPATIER or EBR + GZR for 12 weeks was 97% (64/66).

In C-EDGE TE, a total of 37 genotype 4 treatment-experienced subjects received a 12- or 16-week ZEPATIER with or without RBV regimen. SVR12 among randomized subjects treated with ZEPATIER + RBV for 16 weeks was 100% (8/8).

14.6 Clinical Trial in Pediatric Subjects with Genotype 1 or 4 Chronic Hepatitis C Infection

The efficacy of ZEPATIER was evaluated in an open-label study (MK-5172-079, NCT03379506) that evaluated pediatric subjects 12 years to less than 18 years of age who received ZEPATIER for 12 weeks. HCV GT1a infected subjects with one or more baseline NS5A RAS were excluded from study participation. In the MK-5172-079 study, 22 treatment-naïve or treatment-experienced subjects 12 years to less than 18 years of age with genotype 1 (n=21) or 4 CHC (n=1), without cirrhosis, were treated with ZEPATIER for 12 weeks. The median age was 13.5 years (range: 12 to 17); 50% were female; 95% were White; the weight range was 28.1 kg to 96.5 kg; 95.5% had genotype 1 and 4.5% had genotype 4; 64% were treatment-naïve, 36% were treatment-experienced; 46% had baseline HCV RNA levels greater than 800,000 IU/mL. The overall SVR12 rate was 100% (22/22).

16 HOW SUPPLIED/STORAGE AND HANDLING

Each ZEPATIER tablet contains 50 mg elbasvir and 100 mg grazoprevir, is beige, oval-shaped, film-coated, debossed with "770" on one side and plain on the other. The tablets are packaged into a carton (NDC 0006-3074-02) containing two (2) 14-count child-resistant dose packs for a total of 28 tablets.

STORAGE AND HANDLING

Store ZEPATIER in the original blister package until use to protect from moisture.

Store ZEPATIER at 20°C to 25°C (68°F to 77°F); excursions permitted between 15°C to 30°C (between 59°F to 86°F) [see USP Controlled Room Temperature].

17 PATIENT COUNSELING INFORMATION

Advise the patient to read the FDA-approved patient labeling (Patient Information).

For patients receiving ZEPATIER with ribavirin, advise patients to read the FDA-approved patient labeling (Medication Guide) for ribavirin [see Warnings and Precautions (5.4)].

Risk of Hepatitis B Virus Reactivation in Patients Coinfected with HCV and HBV

Inform patients that HBV reactivation can occur in patients coinfected with HBV during or after treatment of HCV infection. Advise patients to tell their healthcare provider if they have a history of hepatitis B virus infection [see Warnings and Precautions (5.1)].

Risk of Hepatic Decompensation/Failure in Patients with Evidence of Advanced Liver Disease

Advise patients to seek medical evaluation immediately for symptoms of worsening liver problems such as nausea, tiredness, yellowing of the skin or white part of the eyes, bleeding or bruising more easily than normal, confusion, loss of appetite, diarrhea, dark or brown urine, dark or bloody stool, swelling of the stomach area (abdomen) or pain in the upper right side of the stomach area, sleepiness, or vomiting of blood [see Warnings and Precautions (5.3)].

Risk of ALT Elevations

Inform patients to watch for early warning signs of liver inflammation, such as fatigue, weakness, lack of appetite, nausea and vomiting, as well as later signs such as jaundice and discolored feces, and to consult their healthcare professional without delay if such symptoms occur [see Warnings and Precautions (5.2) and Adverse Reactions (6.1)].

Pregnancy

Advise patients taking ZEPATIER with ribavirin to avoid pregnancy during treatment and within 6 months of stopping ribavirin and to notify their healthcare provider immediately in the event of a pregnancy [see Use in Specific Populations (8.1)].

Drug Interactions

Inform patients that ZEPATIER may interact with some drugs; therefore, advise patients to report the use of any prescription, non-prescription medication, or herbal products to their healthcare provider [see Contraindications (4), Warnings and Precautions (5.5), and Drug Interactions (7)].

Storage

Advise patients to store ZEPATIER in the original package until use to protect from moisture [see How Supplied/Storage and Handling (16)].

Administration

Advise patients to take ZEPATIER every day at the regularly scheduled time with or without food. Inform patients that it is important not to miss or skip doses and to take ZEPATIER for the duration that is recommended by the healthcare provider.

Manufactured for: Merck Sharp & Dohme LLC
Rahway, NJ 07065, USA

For patent information: www.msd.com/research/patent

Copyright © 2016-2022 Merck & Co., Inc., Rahway, NJ, USA, and its affiliates.
All rights reserved.

uspi-mk5172a-t-2205r008

Patient Information
ZEPATIER® (ZEP-ah-teer)
(elbasvir and grazoprevir)
tablets

What you need to know about ZEPATIER

- Before you take this medicine, be sure you understand what it is for and how to take it safely.
- Keep this information.
- If you have questions about this medicine, ask your healthcare provider or pharmacist.
- Every time you get a refill, look at the Patient Information. There may be new information.
- Your healthcare provider may prescribe ZEPATIER with a medicine called ribavirin. Ribavirin is also known as Rebetol®, Copegus®, Ribasphere®, and Moderiba®. If you take ZEPATIER and ribavirin, be sure you read the Medication Guide for ribavirin.

What is the most important information I should know about ZEPATIER?

ZEPATIER can cause serious side effects, including,
Hepatitis B virus reactivation: Before starting treatment with ZEPATIER, your healthcare provider will do blood tests to check for hepatitis B virus infection. If you have ever had hepatitis B virus infection, the hepatitis B virus could become active again during or after treatment of hepatitis C virus infection with ZEPATIER. Hepatitis B virus becoming active again (called reactivation) may cause serious liver problems including liver failure and death. Your healthcare provider will monitor you if you are at risk for hepatitis B virus reactivation during treatment and after you stop taking ZEPATIER.

For more information about side effects, see the section "What are the possible side effects of ZEPATIER?"

What is ZEPATIER®?

ZEPATIER is a prescription medicine used with or without ribavirin to treat chronic (long-lasting) hepatitis C virus (HCV) genotypes 1 or 4 infection in adults and children 12 years of age and older or weighing at least 66 pounds (30 kilograms).

ZEPATIER should not be used in children younger than 12 years of age who weigh less than 66 pounds (30 kilograms).

It is not known if ZEPATIER is safe or effective in people awaiting a liver transplant or people who have had a liver transplant.

Who should not take ZEPATIER?

Do not take ZEPATIER if you have certain liver problems.

What should I tell my healthcare provider before taking ZEPATIER?

Before taking ZEPATIER, tell your healthcare provider about all of your medical conditions, including if you:

- have ever had hepatitis B virus infection
- have liver problems other than hepatitis C
- have ever taken any medicine for hepatitis C
- have HIV
- have had or are waiting for a liver transplant
- are pregnant or trying to get pregnant. ZEPATIER has not been studied in pregnant women. We do not know if ZEPATIER will harm your baby while you are pregnant.
  - Males and females who take ZEPATIER and ribavirin should also read the ribavirin Medication Guide for important pregnancy, contraception, and infertility information.
- are breastfeeding or plan to breastfeed. We do not know if ZEPATIER gets in your breast milk and gets passed to your baby.
  - Talk to your healthcare provider about the best way to feed your baby during treatment with ZEPATIER.

Are you taking other medicines?

Tell your healthcare provider about all of the medicines you take, including prescription and over-the-counter medicines, vitamins, and herbal supplements. ZEPATIER may affect the way other medicines work, and other medicines may affect how ZEPATIER works. Some medicines cannot be taken with ZEPATIER. Your healthcare provider can tell you if it is safe to take ZEPATIER with other medicines.

- Know the medicines you take. Keep a list of your medicines and show it to your healthcare provider and pharmacist when you get a new medicine.
- You can ask your healthcare provider or pharmacist for a list of medicines that interact with this medicine.
- Do not start taking a new medicine without telling your healthcare provider.

How do I take ZEPATIER?

- Take 1 ZEPATIER tablet at the same time every day.
- ZEPATIER comes in a blister package of individually-packaged tablets. Keep the tablets in this package until you are ready to take your dose.
- Take ZEPATIER exactly as your healthcare provider tells you to take it.
- Take ZEPATIER with or without food.
- Do not stop taking ZEPATIER without first talking with your healthcare provider.
- If you take more than your prescribed dose, call your healthcare provider right away.

What if I forget to take ZEPATIER?

- Do not take two doses of ZEPATIER at the same time to make up for a missed dose.
- If you are not sure what to do, call your healthcare provider or pharmacist. It is important that you do not miss or skip doses of ZEPATIER during treatment.

What are the possible side effects of ZEPATIER?

ZEPATIER can cause serious side effects, including:
Hepatitis B virus reactivation. See "What is the most important information I should know about ZEPATIER?"

Signs of liver problems. ZEPATIER may cause increases in your liver-related blood tests. This could be a sign of serious liver problems. Your healthcare provider will do blood tests to check your liver before and during treatment with ZEPATIER. Tell your healthcare provider right away if you get any of the following symptoms or if they get worse during treatment with ZEPATIER:

- loss of appetite
- nausea and vomiting
- feeling tired or weak
- confusion
- sleepiness
- vomiting of blood

- yellowing of your skin or eyes
- color changes in your stool or urine
- bleeding or bruising more easily than normal
- diarrhea
- swelling of the stomach area (abdomen) or pain in the upper right side of the stomach area

Common side effects of ZEPATIER when used without ribavirin include:

- feeling tired
- headache
- nausea

- trouble sleeping
- diarrhea

Common side effects of ZEPATIER when used with ribavirin include:

- low red blood cell counts (anemia)
- headache
- feeling tired
- shortness of breath
- rash or itching

- feeling irritable
- stomach pain
- depression
- joint pain

If you have any side effect that bothers you or that does not go away, tell your healthcare provider.

There may be other side effects to ZEPATIER that are not listed.

Call your doctor for medical advice about side effects. You may report side effects to FDA at 1-800-FDA-1088. For more information or medical advice call your doctor.

Where should I keep ZEPATIER?

- Keep ZEPATIER in its original packaging (blister package) until you are ready to take it. Do not take the tablets out of the original blister package to store in another container such as a pill box. This is important because the tablets are sensitive to moisture. The package is designed to protect them.
- Keep ZEPATIER at room temperature.
- Keep ZEPATIER and all medicines out of the reach of children.

General information about ZEPATIER

- Medicines are sometimes prescribed for purposes other than those listed in the patient information. Do not use ZEPATIER for a condition for which it was not prescribed. Do not give ZEPATIER to other people, even if they have the same condition. It may harm them.
- If you would like more information, talk with your healthcare provider or pharmacist. You can ask them for information about ZEPATIER that was written for health professionals.
- For more information, call the company that makes ZEPATIER at 1-877-888-4231 or go to www.ZEPATIER.com.

What are the ingredients in ZEPATIER?

The active ingredients are: elbasvir and grazoprevir.

The inactive ingredients are: colloidal silicon dioxide, copovidone, croscarmellose sodium, hypromellose, lactose monohydrate, magnesium stearate, mannitol, microcrystalline cellulose, sodium chloride, sodium lauryl sulfate, and vitamin E polyethylene glycol succinate.

The tablets are film-coated with a coating material containing the following inactive ingredients: carnauba wax, ferrosoferric oxide, hypromellose, iron oxide red, iron oxide yellow, lactose monohydrate, titanium dioxide, and triacetin.

This Patient Information has been approved by the U.S. Food and Drug Administration.

Manufactured for: Merck Sharp & Dohme LLC
Rahway, NJ 07065, USA

For patent information: www.msd.com/research/patent
The trademarks depicted herein are owned by their respective companies.
Copyright © 2016-2022 Merck & Co., Inc., Rahway, NJ, USA, and its affiliates.
All rights reserved.

Revised: 05/2022
usppi-mk5172a-t-2205r005

PRINCIPAL DISPLAY PANEL - 50 mg/100 mg Tablet Dose Pack Carton

NDC 0006-3074-02

Zepatier®
(elbasvir and grazoprevir) tablets

50 mg/100 mg

Rx only

28 Tablets

This carton contains a total of 28 tablets
packaged within 2 dose packs.
Each dose pack contains 14 blister units
with one tablet per blister unit.